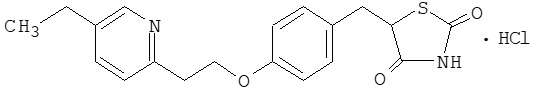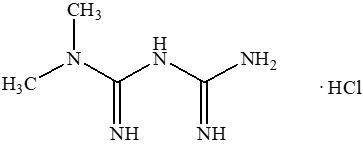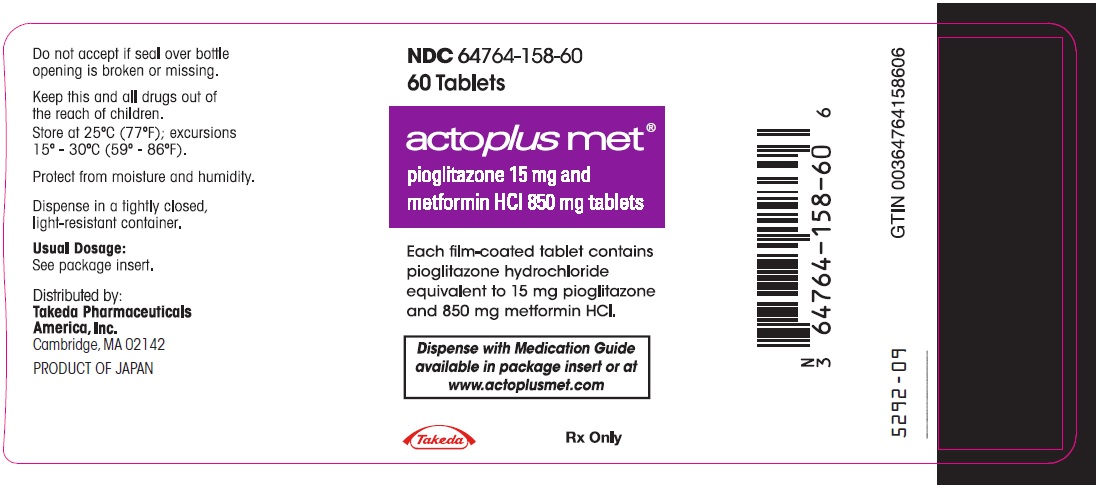 DRUG LABEL: Actoplus Met
NDC: 64764-158 | Form: TABLET, FILM COATED
Manufacturer: Takeda Pharmaceuticals America, Inc.
Category: prescription | Type: HUMAN PRESCRIPTION DRUG LABEL
Date: 20250327

ACTIVE INGREDIENTS: PIOGLITAZONE HYDROCHLORIDE 15 mg/1 1; metformin hydrochloride 850 mg/1 1
INACTIVE INGREDIENTS: POVIDONE, UNSPECIFIED; microcrystalline cellulose; croscarmellose sodium; magnesium stearate; hypromellose 2910 (6 MPA.S); polyethylene glycol 8000; titanium dioxide; talc

HIGHLIGHTS OF PRESCRIBING INFORMATION

These highlights do not include all the information needed to use ACTOPLUS MET® safely and effectively. See full prescribing information for ACTOPLUS MET.
ACTOPLUS MET (pioglitazone and metformin hydrochloride) tablets, for oral use
Initial U.S. Approval: 2005

WARNING: CONGESTIVE HEART FAILURE and LACTIC ACIDOSIS

See full prescribing information for complete boxed warning.

Congestive Heart Failure

- Thiazolidinediones, including pioglitazone, which is a component of ACTOPLUS MET, cause or exacerbate congestive heart failure in some patients. (5.1)
- After initiation of ACTOPLUS MET, and after dose increases, monitor patients carefully for signs and symptoms of heart failure (e.g., excessive, rapid weight gain, dyspnea, and/or edema). If congestive heart failure develops while taking ACTOPLUS MET, consider discontinuation of ACTOPLUS MET or dosage reduction of pioglitazone in ACTOPLUS MET. (5.1)
- ACTOPLUS MET is not recommended in patients with symptomatic heart failure. (5.1)
- Initiation of ACTOPLUS MET in patients with established New York Heart Association (NYHA) Class III or IV heart failure is contraindicated. (4, 5.1)

Lactic Acidosis

- Postmarketing cases of metformin-associated lactic acidosis have resulted in death, hypothermia, hypotension, and resistant bradyarrhythmias. Symptoms included malaise, myalgias, respiratory distress, somnolence, and abdominal pain. Laboratory abnormalities included elevated blood lactate levels, anion gap acidosis, increased lactate:pyruvate ratio; and metformin plasma levels generally greater than 5 mcg/mL. (5.2)
- Risk factors include renal impairment, concomitant use of certain drugs, age ≥65 years old, radiological studies with contrast, surgery and other procedures, hypoxic states, excessive alcohol intake, and hepatic impairment. Steps to reduce the risk of and manage metformin-associated lactic acidosis in these high-risk groups are provided in the Full Prescribing Information. (5.2)
- If lactic acidosis is suspected, discontinue ACTOPLUS MET and institute general supportive measures in a hospital setting. Prompt hemodialysis is recommended. (5.2)

RECENT MAJOR CHANGES

Dosage and Administration

Important Dosage and Administration Information (2.1) | 06/2024
Recommended Dosage and Administration (2.2) | 06/2024
Recommendations for Use in Patients with Renal Impairment (2.3) | 06/2024
Recommendations for Congestive Heart Failure (2.4) | 06/2024
Coadministration with Strong CYP2C8 Inhibitors (2.5) | 06/2024

1 INDICATIONS AND USAGE

ACTOPLUS MET is a combination of pioglitazone, a thiazolidinedione agonist of peroxisome proliferator receptor gamma, and metformin hydrochloride (HCl), a biguanide, indicated as an adjunct to diet and exercise to improve glycemic control in adults with type 2 diabetes mellitus. (1)

Limitations of Use:

Not recommended for treatment of type 1 diabetes or diabetic ketoacidosis. (1)

2 DOSAGE AND ADMINISTRATION

- Obtain liver tests before initiation. If abnormal, use caution when treating with ACTOPLUS MET, investigate the probable cause, treat (if possible), and follow appropriately. (2.1)
- Take orally with meals to reduce gastrointestinal adverse reactions with metformin (2.10)
- Individualize the starting dose based on the patient’s current regimen and titrate the dosage gradually, as needed after assessing therapeutic response and tolerability. The maximum recommended total daily dosage is pioglitazone 45 mg and metformin 2,550 mg. (2.2)
- Recommended starting dosage in patients with NYHA Class I or Class II congestive heart failure is 15 mg of pioglitazone and 850 mg of metformin HCl orally once daily. (2.4)
- Prior to initiation, assess renal function with estimated glomerular filtration rate (eGFR). (2.2)
  - Contraindicated in patients with eGFR below 30 mL/min
  - Initiation is not recommended in patients with eGFR between 30 to 45 mL/min
  - Assess risk/benefit of continuing ACTOPLUS MET if eGFR falls below 45 mL/min
  - Discontinue if eGFR falls below 30 mL/min
- Monitor patients for adverse events related to fluid retention after initiation and dose increases. (2.4)
- ACTOPLUS MET may need to be discontinued at time of, or prior to, iodinated contrast imaging procedures. (2.6)

3 DOSAGE FORMS AND STRENGTHS

Tablets: 15 mg pioglitazone/850 mg metformin HCl. (3)

4 CONTRAINDICATIONS

- In patients with established New York Heart Association (NYHA) Class III or IV heart failure at the time of ACTOPLUS MET initiation [see Boxed Warning]. (4)
- In patients with severe renal impairment: (eGFR below 30 mL/min). (4)
- In patients with a history of serious hypersensitivity to pioglitazone, metformin HCl, or any of the excipients in ACTOPLUS MET. (4)
- In patients with acute or chronic metabolic acidosis, including diabetic ketoacidosis. (4)

5 WARNINGS AND PRECAUTIONS

- Congestive heart failure: Fluid retention may occur and can exacerbate or lead to congestive heart failure. Combination use with insulin and use in congestive heart failure NYHA Class I and II may increase risk. Monitor patients for signs and symptoms. (5.1)
- Edema: Dose-related edema may occur. (5.3)
- Hypoglycemia: Consider a lower dose of insulin or insulin secretagogue to reduce risk of hypoglycemia when used in combination with ACTOPLUS MET. (5.4)
- Hepatic effects: Postmarketing reports of hepatic failure, sometimes fatal. Causality cannot be excluded. If liver injury is detected, promptly interrupt ACTOPLUS MET and assess patient for probable cause, then treat cause if possible, to resolution or stabilization. Do not restart ACTOPLUS MET if liver injury is confirmed and no alternate etiology can be found. (5.5)
- Urinary Bladder Tumors: May increase the risk of bladder cancer. Do not use in patients with active bladder cancer. Use caution when using in patients with a prior history of bladder cancer. (5.6)
- Fractures: Increased incidence in female patients. Apply current standards of care for assessing and maintaining bone health. (5.7)
- Macular edema: Postmarketing reports. Recommend regular eye exams in all patients with diabetes according to current standards of care with prompt evaluation for acute visual changes. (5.8)
- Vitamin B12 deficiency: Metformin may lower vitamin B12 levels. Monitor hematologic parameters annually and vitamin B12 at 2 to 3 year intervals and manage any abnormalities. (5.9)

6 ADVERSE REACTIONS

Most common adverse reactions (>5%) are upper respiratory tract infection, edema, diarrhea, headache and weight gain. (6.1)

To report SUSPECTED ADVERSE REACTIONS, contact Takeda Pharmaceuticals America, Inc. at 1-877-825-3327 and the ACTOPLUS MET website at: www.actoplusmet.com or FDA at 1-800-FDA-1088 or www.fda.gov/medwatch.

7 DRUG INTERACTIONS

- Strong CYP2C8 inhibitors (e.g., gemfibrozil): Limit ACTOPLUS MET dose to 15 mg/850 mg daily. (7.1)
- CYP2C8 inducers (e.g., rifampin) may decrease pioglitazone concentrations. (7.2)
- Carbonic anhydrase inhibitors may increase risk of lactic acidosis. Consider more frequent monitoring. (7.3)
- Drugs that reduce metformin clearance (such as ranolazine, vandetanib, dolutegravir, and cimetidine), may increase the accumulation of metformin. Consider the benefits and risks of concomitant use. (7.4)
- Alcohol: Warn patients against excessive alcohol intake. (7.5)
- Use of insulin secretagogues or insulin use may increase the risk for hypoglycemia and may require dose reduction. (7.6)
- Topiramate may decrease pioglitazone concentrations. (7.8)

8 USE IN SPECIFIC POPULATIONS

- Females and Males of Reproductive Potential: Advise premenopausal females of the potential for an unintended pregnancy. (8.3)
- Pediatrics: Safety and effectiveness have not been established. (8.4)
- Geriatric Use: Assess renal function more frequently. (8.5)
- Hepatic Impairment: Avoid use in patients with hepatic impairment. (8.7)

FULL PRESCRIBING INFORMATION

WARNING: CONGESTIVE HEART FAILURE and LACTIC ACIDOSIS

Congestive Heart Failure

- Thiazolidinediones, including pioglitazone, which is a component of ACTOPLUS MET®, cause or exacerbate congestive heart failure in some patients [see Warnings and Precautions (5.1)].
- After initiation of ACTOPLUS MET, and after dose increases, monitor patients carefully for signs and symptoms of heart failure (e.g., excessive, rapid weight gain, dyspnea, and/or edema). If congestive heart failure develops while taking ACTOPLUS MET, consider discontinuation of ACTOPLUS MET or dosage reduction of pioglitazone in ACTOPLUS MET [see Warnings and Precautions (5.1)].
- ACTOPLUS MET is not recommended in patients with symptomatic heart failure [see Warnings and Precautions (5.1)].
- Initiation of ACTOPLUS MET in patients with established New York Heart Association (NYHA) Class III or IV heart failure is contraindicated [see Contraindications (4), Warnings and Precautions (5.1)].

Lactic Acidosis

- Postmarketing cases of metformin-associated lactic acidosis have resulted in death, hypothermia, hypotension, and resistant bradyarrhythmias. The onset of metformin-associated lactic acidosis is often subtle, accompanied only by nonspecific symptoms such as malaise, myalgias, respiratory distress, somnolence, and abdominal pain. Metformin-associated lactic acidosis was characterized by elevated blood lactate levels (greater than 5 mmol/L), anion gap acidosis (without evidence of ketonuria or ketonemia), an increased lactate:pyruvate ratio; and metformin plasma levels generally greater than 5 mcg/mL [see Warnings and Precautions (5.2)].
- Risk factors for metformin-associated lactic acidosis include renal impairment, concomitant use of certain drugs (e.g., carbonic anhydrase inhibitors such as topiramate), age 65 years old or greater, having a radiological study with contrast, surgery and other procedures, hypoxic states (e.g., acute congestive heart failure), excessive alcohol intake, and hepatic impairment.
- Steps to reduce the risk of and manage metformin-associated lactic acidosis in these high-risk groups are provided in the Full Prescribing Information [see Dosage and Administration (2.2), Contraindications (4), Warnings and Precautions (5.2), Drug Interactions (7), Use in Specific Populations (8.6, 8.7)].
- If metformin-associated lactic acidosis is suspected, immediately discontinue ACTOPLUS MET and institute general supportive measures in a hospital setting. Prompt hemodialysis is recommended [see Warnings and Precautions (5.2)].

1 INDICATIONS AND USAGE

ACTOPLUS MET is indicated as an adjunct to diet and exercise to improve glycemic control in adults with type 2 diabetes mellitus.

Limitations of Use

ACTOPLUS MET is not recommended to treat type 1 diabetes mellitus or diabetic ketoacidosis.

2 DOSAGE AND ADMINISTRATION

2.1 Important Dosage and Administration Information

- Obtain liver tests (serum alanine and aspartate aminotransferases, alkaline phosphatase, and total bilirubin) prior to initiating ACTOPLUS MET [see Warnings and Precautions (5.5)].
- ACTOPLUS MET contains 15 mg of pioglitazone and 850 mg of metformin hydrochloride (HCl) in each tablet.
- Take ACTOPLUS MET with meals to reduce gastrointestinal adverse reactions with metformin [see Adverse Reactions (6.1)].
- If a dose is missed, do not double the next dose.

2.2 Recommended Dosage and Administration

Recommended Starting Dosage Based on Current Regimen

Individualize the starting dosage of ACTOPLUS MET based on the patient's current regimen and the available strength of ACTOPLUS MET (see Table 1).

Table 1: Recommended Starting Dosage Based on the Patient’s Current Regimen
Current Regimen | Starting Dosage of ACTOPLUS MET (15 mg of pioglitazone and 850 mg of metformin HCl per tablet) [For dosage recommendations for patients with renal impairment and/or congestive heart failure, see Dosage and Administration (2.3, 2.4)]
Not treated with either pioglitazone or metformin HCl | One tablet orally once daily
Metformin HCl | One tablet orally once or twice daily. Select a dosage that is as close as possible to the current dosage of metformin HCl
Pioglitazone | One tablet orally once daily
Pioglitazone and metformin HCl | Select a dosage that is as close as possible to the current dosage of pioglitazone and metformin HCl while not exceeding three tablets orally per day.

Dosage Titration for Additional Glycemic Control

Titrate the ACTOPLUS MET dosage gradually, as needed, after assessing therapeutic response and tolerability.

ACTOPLUS MET may be increased to a maximum recommended total daily dosage of three tablets per day (45 mg of pioglitazone and 2,550 mg of metformin HCl). Total daily dosages of 2,550 mg of metformin HCl may be taken in divided doses three times a day to reduce gastrointestinal adverse reactions [see Adverse Reactions (6.1)].

2.3 Recommendations for Use in Patients with Renal Impairment

- Assess renal function prior to initiation of ACTOPLUS MET and periodically thereafter [see Use in Specific Populations (8.6)].
- ACTOPLUS MET is contraindicated in patients with an estimated glomerular filtration rate (eGFR) below 30 mL/min.
- Initiation of ACTOPLUS MET in patients with an eGFR between 30 to 45 mL/min is not recommended.
- In patients taking ACTOPLUS MET whose eGFR later falls below 45 mL/min, assess the benefit and risk of continuing therapy.
- Discontinue ACTOPLUS MET if the patient’s eGFR later falls below 30 mL/min [see Contraindications (4), Warnings and Precautions (5.2)].

2.4 Recommendations for Congestive Heart Failure

Starting Dosage in Patients with NYHA Class I or II Congestive Heart Failure

For patients with preexisting NYHA Class I or II congestive heart failure, the recommended starting dosage of ACTOPLUS MET is 15 mg of pioglitazone and 850 mg of metformin [see Boxed Warning and Warnings and Precautions (5.1)].

Monitoring for Fluid Retention and Dosage Modifications for Congestive Heart Failure

After initiation of ACTOPLUS MET or with dosage increase, monitor patients carefully for adverse reactions related to fluid retention as has been seen with pioglitazone (e.g., weight gain, edema and signs and symptoms of congestive heart failure).

If congestive heart failure develops while taking ACTOPLUS MET, consider discontinuation of ACTOPLUS MET or dosage reduction of pioglitazone in ACTOPLUS MET [see Boxed Warning and Warnings and Precautions (5.1)].

2.5 Coadministration with Strong CYP2C8 Inhibitors

The maximum recommended dosage of ACTOPLUS MET is one tablet (15 mg of pioglitazone and 850 mg of metformin HCl) once daily when used in combination with gemfibrozil or other strong CYP2C8 inhibitors [see Drug Interactions (7.1), Clinical Pharmacology (12.3)].

2.6 Discontinuation for Iodinated Contrast Imaging Procedures

Discontinue ACTOPLUS MET at the time of, or prior to, an iodinated contrast imaging procedure in patients with an eGFR between 30 and 60 mL/min; in patients with a history of liver disease, alcoholism, or heart failure; or in patients who will be administered intra-arterial iodinated contrast. Re-evaluate eGFR 48 hours after the imaging procedure; restart ACTOPLUS MET if renal function is stable [see Warnings and Precautions (5.2)].

3 DOSAGE FORMS AND STRENGTHS

- 15 mg of pioglitazone and 850 mg of metformin HCl tablets: White to off-white, oblong, film-coated tablets debossed with “4833M” on one side and “15/850” on the other

4 CONTRAINDICATIONS

ACTOPLUS MET is contraindicated in patients with:

- Established NYHA Class III or IV heart failure at the time of ACTOPLUS MET initiation [see Boxed Warning].
- Severe renal impairment (eGFR below 30 mL/min) [see Warnings and Precautions (5.2)].
- A history of serious hypersensitivity to pioglitazone, metformin HCl, or any of the excipients in ACTOPLUS MET.
- Acute or chronic metabolic acidosis, including diabetic ketoacidosis [see Warnings and Precautions (5.2)].

5 WARNINGS AND PRECAUTIONS

5.1 Congestive Heart Failure

Pioglitazone, like other thiazolidinediones, can cause dose-related fluid retention when used alone or in combination with other antidiabetic medications and is most common when pioglitazone is used in combination with insulin. Fluid retention may lead to or exacerbate congestive heart failure. Observe patients for signs and symptoms of congestive heart failure. If congestive heart failure develops while taking ACTOPLUS MET, consider discontinuation of ACTOPLUS MET or dosage reduction of pioglitazone in ACTOPLUS MET [see Boxed Warning, Contraindications (4), Adverse Reactions (6.1)].

5.2 Lactic Acidosis

Lactic Acidosis

There have been postmarketing cases of metformin-associated lactic acidosis, including fatal cases. These cases had a subtle onset and were accompanied by nonspecific symptoms such as malaise, myalgias, abdominal pain, respiratory distress, or increased somnolence; however, hypothermia, hypotension and resistant bradyarrhythmias have occurred with severe acidosis. Metformin-associated lactic acidosis was characterized by elevated blood lactate concentrations (greater than 5 mmol/L), anion gap acidosis (without evidence of ketonuria or ketonemia), an increased lactate:pyruvate ratio, and metformin plasma levels generally greater than 5 mcg/mL. Metformin decreases liver uptake of lactate increasing lactate blood levels which may increase the risk of lactic acidosis, especially in patients at risk.

If metformin-associated lactic acidosis is suspected, general supportive measures should be instituted promptly in a hospital setting, along with immediate discontinuation of ACTOPLUS MET. In ACTOPLUS MET-treated patients with a diagnosis or strong suspicion of lactic acidosis, prompt hemodialysis is recommended to correct the acidosis and remove accumulated metformin (metformin HCl is dialyzable, with a clearance of up to 170 mL/min under good hemodynamic conditions). Hemodialysis has often resulted in reversal of symptoms and recovery.

Educate patients and their families about the symptoms of lactic acidosis and if these symptoms occur instruct them to discontinue ACTOPLUS MET and report these symptoms to their healthcare provider.

For each of the known and possible risk factors for metformin-associated lactic acidosis, recommendations to reduce the risk of and manage metformin-associated lactic acidosis are provided below:

Renal Impairment

The postmarketing metformin-associated lactic acidosis cases primarily occurred in patients with significant renal impairment. The risk of metformin accumulation and metformin-associated lactic acidosis increases with the severity of renal impairment because metformin is substantially excreted by the kidney. Clinical recommendations based upon the patient’s renal function include [see Dosage and Administration (2.3), Clinical Pharmacology (12.3)].

- Before initiating ACTOPLUS MET, obtain an eGFR.
- ACTOPLUS MET is contraindicated in patients with an eGFR less than 30 mL/min. Initiation of ACTOPLUS MET is not recommended in patients with eGFR between 30 to 45 mL/min [see Contraindications (4)].
- Obtain an eGFR at least annually in all patients taking ACTOPLUS MET. In patients at increased risk for the development of renal impairment (e.g., the elderly), renal function should be assessed more frequently.
- In patients taking ACTOPLUS MET whose eGFR later falls below 45 mL/min, assess the benefit and risk of continuing therapy.

Drug Interactions

The concomitant use of ACTOPLUS MET with specific drugs may increase the risk of metformin-associated lactic acidosis: those that impair renal function, result in significant hemodynamic change, interfere with acid-base balance or increase metformin accumulation (e.g., cationic drugs) [see Drug Interactions (7)]. Therefore, consider more frequent monitoring of patients.

Age 65 or Greater

The risk of metformin-associated lactic acidosis increases with the patient’s age because elderly patients have a greater likelihood of having hepatic, renal, or cardiac impairment than younger patients. Assess renal function more frequently in elderly patients [see Use in Specific Populations (8.5)].

Radiological Studies with Contrast

Administration of intravascular iodinated contrast agents in metformin-treated patients has led to an acute decrease in renal function and the occurrence of lactic acidosis. Stop ACTOPLUS MET at the time of, or prior to, an iodinated contrast imaging procedure in patients with an eGFR between 30 and 60 mL/min; in patients with a history of hepatic impairment, alcoholism, or heart failure; or in patients who will be administered intra-arterial iodinated contrast. Re-evaluate eGFR 48 hours after the imaging procedure, and restart ACTOPLUS MET if renal function is stable.

Surgery and Other Procedures

Withholding of food and fluids during surgical or other procedures may increase the risk for volume depletion, hypotension and renal impairment. ACTOPLUS MET should be temporarily discontinued while patients have restricted food and fluid intake.

Hypoxic States

Several of the postmarketing cases of metformin-associated lactic acidosis occurred in the setting of acute congestive heart failure (particularly when accompanied by hypoperfusion and hypoxemia). Cardiovascular collapse (shock), acute myocardial infarction, sepsis, and other conditions associated with hypoxemia have been associated with lactic acidosis and may also cause prerenal azotemia. When such events occur, discontinue ACTOPLUS MET.

Excessive Alcohol Intake

Alcohol potentiates the effect of metformin on lactate metabolism and this may increase the risk of metformin-associated lactic acidosis. Warn patients against excessive alcohol intake while receiving ACTOPLUS MET.

Hepatic Impairment

Patients with hepatic impairment have developed with cases of metformin-associated lactic acidosis. This may be due to impaired lactate clearance resulting in higher lactate blood levels. Therefore, avoid use of ACTOPLUS MET in patients with clinical or laboratory evidence of hepatic disease.

5.3 Edema

In controlled clinical trials with pioglitazone, edema was reported more frequently in patients treated with pioglitazone than in placebo-treated patients and is dose related [see Adverse Reactions (6.1)]. In postmarketing experience, reports of new onset or worsening of edema have been received.

ACTOPLUS MET should be used with caution in patients with edema. Because thiazolidinediones, including pioglitazone, can cause fluid retention, which can exacerbate or lead to congestive heart failure, ACTOPLUS MET should be used with caution in patients at risk for congestive heart failure. Patients treated with ACTOPLUS MET should be monitored for signs and symptoms of congestive heart failure [see Boxed Warning, Warnings and Precautions (5.1)].

5.4 Hypoglycemia with Concomitant Use with Insulin or Insulin Secretagogues

Insulin and insulin secretagogues, such as sulfonylureas, are known to cause hypoglycemia. Therefore, a lower dosage of insulin or insulin secretagogue may be required to minimize the risk of hypoglycemia when used in combination with ACTOPLUS MET [see Drug Interactions (7.6, 7.7)].

5.5 Hepatic Effects

There have been postmarketing reports of fatal and non-fatal hepatic failure in patients taking pioglitazone, although the reports contain insufficient information necessary to establish the probable cause. There has been no evidence of drug-induced hepatotoxicity in the pioglitazone controlled clinical trial database to date [see Adverse Reactions (6.1)].

Patients with type 2 diabetes mellitus may have fatty liver disease or cardiac disease with episodic congestive heart failure, both of which may cause liver test abnormalities, and they may also have other forms of liver disease, many of which can be treated or managed. Therefore, obtaining a liver test panel (serum alanine aminotransferase [ALT], aspartate aminotransferase [AST], alkaline phosphatase, and total bilirubin) and assessing the patient is recommended before initiating ACTOPLUS MET therapy. In patients with abnormal liver tests, ACTOPLUS MET should be initiated with caution.

Measure liver tests promptly in patients who report symptoms that may indicate liver injury, including fatigue, anorexia, right upper abdominal discomfort, dark urine or jaundice. In this clinical context, if the patient is found to have clinically significant liver enzyme elevations (serum ALT greater than three times the ULN) and if abnormal liver tests persist or worsen, ACTOPLUS MET should be interrupted and investigation done to establish the probable cause. ACTOPLUS MET should not be restarted in these patients without another explanation for the liver test abnormalities.

5.6 Urinary Bladder Tumors

Tumors were observed in the urinary bladder of male rats in the two year carcinogenicity study [see Nonclinical Toxicology (13.1)]. In addition, during the three year PROactive clinical trial, 14 patients out of 2,605 (0.54%) randomized to pioglitazone and 5 out of 2,633 (0.19%) randomized to placebo were diagnosed with bladder cancer. After excluding patients in whom exposure to study drug was less than one year at the time of diagnosis of bladder cancer, there were 6 (0.23%) cases on pioglitazone and 2 (0.08%) cases on placebo. After completion of the trial, a large subset of patients was observed for up to 10 additional years, with little additional exposure to pioglitazone. During the 13 years of both PROactive and observational follow-up, the occurrence of bladder cancer did not differ between patients randomized to pioglitazone or placebo [Hazard Ratio (HR) = 1.00; (95% Confidence Interval (CI) : 0.59, 1.72)].

Findings regarding the risk of bladder cancer in patients exposed to pioglitazone vary among observational studies; some did not find an increased risk of bladder cancer associated with pioglitazone, while others did.

A large prospective10 year observational cohort study conducted in the United States (U.S) found no statistically significant increase in the risk of bladder cancer in diabetic patients ever exposed to pioglitazone, compared to those never exposed to pioglitazone [HR = 1.06; (95% CI: 0.89, 1.26)].

A retrospective cohort study conducted with data from the United Kingdom found a statistically significant association between ever exposure to pioglitazone and bladder cancer [HR = 1.63; (95% CI: 1.22, 2.19)].

Associations between cumulative dose or cumulative duration of exposure to pioglitazone and bladder cancer were not detected in some studies including the 10 year observational study in the U.S., but were in others. Inconsistent findings and limitations inherent in these and other studies preclude conclusive interpretations of the observational data.

Pioglitazone may be associated with an increase in the risk of urinary bladder tumors. There are insufficient data to determine whether pioglitazone is a tumor promoter for urinary bladder tumors.

Consequently, ACTOPLUS MET should not be used in patients with active bladder cancer and the benefits of glycemic control versus unknown risks for cancer recurrence with ACTOPLUS MET should be considered in patients with a prior history of bladder cancer.

5.7 Fractures

In PROactive (the Prospective Pioglitazone Clinical Trial in Macrovascular Events), 5,238 patients with type 2 diabetes mellitus and a history of macrovascular disease were randomized to pioglitazone (N=2,605), force-titrated up to 45 mg daily or placebo (N=2,633) in addition to standard of care. During a mean follow-up of 34.5 months, the incidence of bone fracture in females was 5.1% (44/870) for pioglitazone versus 2.5% (23/905) for placebo. This difference was noted after the first year of treatment and persisted during the course of the study. The majority of fractures observed in female patients were nonvertebral fractures including lower limb and distal upper limb. No increase in the incidence of fracture was observed in men treated with pioglitazone (1.7%) versus placebo (2.1%). The risk of fracture should be considered in the care of patients, especially female patients, treated with ACTOPLUS MET and attention should be given to assessing and maintaining bone health according to current standards of care.

5.8 Macular Edema

Macular edema has been reported in postmarketing experience in diabetic patients who were taking pioglitazone or another thiazolidinedione. Some patients presented with blurred vision or decreased visual acuity, but others were diagnosed on routine ophthalmologic examination.

Most patients had peripheral edema at the time macular edema was diagnosed. Some patients had improvement in their macular edema after discontinuation of the thiazolidinedione.

Patients with diabetes should have regular eye exams by an ophthalmologist according to current standards of care. Patients with diabetes who report any visual symptoms should be promptly referred to an ophthalmologist, regardless of the patient's underlying medications or other physical findings [see Adverse Reactions (6.1)].

5.9 Vitamin B12 Levels

In metformin clinical trials of 29-week duration, a decrease to subnormal levels of previously normal serum vitamin B12 levels was observed in approximately 7% of patients. Such decrease, possibly due to interference with B12 absorption from the B12-intrinsic factor complex, may be associated with anemia but appears to be rapidly reversible with discontinuation of metformin or vitamin B12 supplementation. Certain individuals (those with inadequate vitamin B12 or calcium intake or absorption) appear to be predisposed to developing subnormal vitamin B12 levels. Measure hematologic parameters on an annual basis and vitamin B12 at 2 to 3 year intervals in patients on ACTOPLUS MET and manage any abnormalities [see Adverse Reactions (6.1)].

6 ADVERSE REACTIONS

The following serious adverse reactions are discussed elsewhere in the labeling:

- Congestive heart failure [see Boxed Warning, Warnings and Precautions (5.1)]
- Lactic acidosis [see Boxed Warning, Warnings and Precautions (5.2)]
- Edema [see Warnings and Precautions (5.3)]
- Hypoglycemia with Concomitant Use with Insulin or Insulin Secretagogues [see Warnings and Precautions (5.4)]
- Hepatic Effects [see Warnings and Precautions (5.5)]
- Urinary Bladder Tumors [see Warnings and Precautions (5.6)]
- Fractures [see Warnings and Precautions (5.7)]
- Macular Edema [see Warnings and Precautions (5.8]
- Vitamin B12 Levels [see Warnings and Precautions (5.9]

6.1 Clinical Trials Experience

Because clinical trials are conducted under widely varying conditions, adverse reaction rates observed in the clinical trials of a drug cannot be directly compared to rates in the clinical trials of another drug and may not reflect the rates observed in practice.

Pioglitazone

Over 8,500 patients with type 2 diabetes mellitus have been treated with pioglitazone in randomized, double-blind, controlled clinical trials, including 2,605 patients with type 2 diabetes mellitus and macrovascular disease treated with pioglitazone from the PROactive clinical trial. In these trials, over 6,000 patients have been treated with pioglitazone for six months or longer, over 4,500 patients have been treated with pioglitazone for one year or longer, and over 3,000 patients have been treated with pioglitazone for at least two years.

In six pooled 16 to 26 week placebo-controlled monotherapy and 16 to 24 week add-on combination therapy trials, the incidence of withdrawals due to adverse events was 4.5% for patients treated with pioglitazone and 5.8% for comparator-treated patients. The most common adverse events leading to withdrawal were related to inadequate glycemic control, although the incidence of these events was lower (1.5%) with pioglitazone than with placebo (3.0%).

In the PROactive trial, the incidence of withdrawals due to adverse events was 9.0% for patients treated with pioglitazone and 7.7% for placebo-treated patients. Congestive heart failure was the most common serious adverse event leading to withdrawal occurring in 1.3% of patients treated with pioglitazone and 0.6% of patients treated with placebo.

Common Adverse Events: 16 to 26 Week Monotherapy Trials

A summary of the incidence and type of common adverse events reported in three pooled 16 to 26 week placebo-controlled monotherapy trials of pioglitazone is provided in Table 2. Terms that are reported represent those that occurred at an incidence of >5% and more commonly in patients treated with pioglitazone than in patients who received placebo. None of these adverse events were related to the pioglitazone dose.

Table 2: Three Pooled 16 to 26 Week Placebo-Controlled Clinical Trials of Pioglitazone Monotherapy: Adverse Events Reported at an Incidence >5% and More Commonly in Patients Treated with Pioglitazone than in Patients Treated with Placebo
% of Patients
 | Placebo N=259 | Pioglitazone N=606
Upper Respiratory Tract Infection | 8.5 | 13.2
Headache | 6.9 | 9.1
Sinusitis | 4.6 | 6.3
Myalgia | 2.7 | 5.4
Pharyngitis | 0.8 | 5.1

Common Adverse Events: 16 to 24 Week Add-on Combination Therapy Trials

A summary of the overall incidence and types of common adverse events reported in trials of pioglitazone add-on to metformin is provided in Table 3. Terms that are reported represent those that occurred at an incidence of >5% and more commonly with the highest tested dose of pioglitazone.

Table 3: 16 to 24 Week Clinical Trials of Pioglitazone Add-on to Metformin
 | 16 Week Placebo-Controlled Trial Adverse Events Reported in >5% of Patients and More Commonly in Patients Treated with Pioglitazone + Metformin than in Patients Treated with Placebo + Metformin
 | % of Patients
 | Placebo + Metformin N=160 | Pioglitazone 30 mg + Metformin N=168
Edema | 2.5 | 6.0
Headache | 1.9 | 6.0
 | 24 Week Non-Controlled Double-Blind Trial Adverse Events Reported in >5% of Patients and More Commonly in Patients Treated with Pioglitazone 45 mg + Metformin than in Patients Treated with Pioglitazone 30 mg + Metformin
 | % of Patients
 | Pioglitazone 30 mg + Metformin N=411 | Pioglitazone 45 mg + Metformin N=416
Upper Respiratory Tract Infection | 12.4 | 13.5
Edema | 5.8 | 13.9
Headache | 5.4 | 5.8
Weight Increased | 2.9 | 6.7
Note: The preferred terms of edema peripheral, generalized edema, pitting edema, and fluid retention were combined to form the aggregate term of “edema.”

Common Adverse Events: 24 Week ACTOPLUS MET Clinical Trial

Table 4 summarizes the incidence and types of adverse reactions reported in a controlled, 24 week double-blind clinical trial of ACTOPLUS MET dosed twice daily in patients with inadequate glycemic control on diet and exercise (N=600).

Table 4: Adverse Events (≥5% for ACTOPLUS MET) Reported by Patients with Inadequate Glycemic Control on Diet and Exercise in a 24 Week Double-Blind Clinical Trial of ACTOPLUS MET Administered Twice Daily
% of Patients
 | ACTOPLUS MET 15/850 mg Twice Daily N=201 | Pioglitazone 15 mg Twice Daily N=190 | Metformin 850 mg Twice Daily N=209
Diarrhea | 9.0 | 2.6 | 15.3
Headache | 5.5 | 2.6 | 4.8

In this 24 week trial, abdominal pain was reported in 2.0% of patients in the ACTOPLUS MET group, 1.6% in the pioglitazone monotherapy group and 3.3% in the metformin monotherapy group.

Common Adverse Events: PROactive Trial

A summary of the overall incidence and types of common adverse events reported in the PROactive trial is provided in Table 5. Terms that are reported represent those that occurred at an incidence of >5% and more commonly in patients treated with pioglitazone than in patients who received placebo.

Table 5: PROactive Trial: Incidence and Types of Adverse Events Reported in >5% of Patients Treated with Pioglitazone and More Commonly than Placebo
 | % of Patients
 | Placebo N=2,633 | Pioglitazone N=2,605
Hypoglycemia | 18.8 | 27.3
Edema | 15.3 | 26.7
Cardiac Failure | 6.1 | 8.1
Pain in Extremity | 5.7 | 6.4
Back Pain | 5.1 | 5.5
Chest Pain | 5.0 | 5.1
Mean duration of patient follow-up was 34.5 months.

Congestive Heart Failure

A summary of the incidence of adverse events related to congestive heart failure is provided in Table 6 for the 16 to 24 week add-on to metformin trials. None of the events were fatal.

Table 6: Treatment-Emergent Adverse Events of Congestive Heart Failure (CHF) Patients Treated with Pioglitazone or Placebo Added on to Metformin
 | Number (%) of Patients
 | Placebo-Controlled Trial (16 weeks) |  | Non-Controlled Double-Blind Trial (24 weeks)
 | Placebo + Metformin N=160 | Pioglitazone 30 mg + Metformin N=168 | Pioglitazone 30 mg + Metformin N=411 | Pioglitazone 45 mg + Metformin N=416
At least one congestive heart failure event | 0 | 1 (0.6%) | 0 | 1 (0.2%)
Hospitalized | 0 | 1 (0.6%) | 0 | 1 (0.2%)

Table 7: Treatment-Emergent Adverse Events of Congestive Heart Failure (CHF)
Patients Treated with Pioglitazone or Placebo Added on to a Sulfonylurea
 | Number (%) of Patients
 | Placebo-Controlled Trial (16 weeks) |  |  | Non-Controlled Double-Blind Trial (24 weeks)
 | Placebo + Sulfonylurea N=187 | Pioglitazone 15 mg + Sulfonylurea N=184 | Pioglitazone 30 mg + Sulfonylurea N=189 | Pioglitazone 30 mg + Sulfonylurea N=351 | Pioglitazone 45 mg + Sulfonylurea N=351
At least one congestive heart failure event | 2 (1.1%) | 0 | 0 | 1 (0.3%) | 6 (1.7%)
Hospitalized | 2 (1.1%) | 0 | 0 | 0 | 2 (0.6%)
Patients Treated with Pioglitazone or Placebo Added on to Insulin
 | Number (%) of Patients
 | Placebo-Controlled Trial (16 weeks) |  |  | Non-Controlled Double-Blind Trial (24 weeks)
 | Placebo + Insulin N=187 | Pioglitazone 15 mg + Insulin N=191 | Pioglitazone 30 mg + Insulin N=188 | Pioglitazone 30 mg + Insulin N=345 | Pioglitazone 45 mg + Insulin N=345
At least one congestive heart failure event | 0 | 2 (1.0%) | 2 (1.1%) | 3 (0.9%) | 5 (1.4%)
Hospitalized | 0 | 2 (1.0%) | 1 (0.5%) | 1 (0.3%) | 3 (0.9%)
Patients Treated with Pioglitazone or Placebo Added on to Metformin
 | Number (%) of Patients
 | Placebo-Controlled Trial (16 weeks) |  |  | Non-Controlled Double-Blind Trial (24 weeks)
 | Placebo + Metformin N=160 | Pioglitazone 30 mg + Metformin N=168 |  | Pioglitazone 30 mg + Metformin N=411 | Pioglitazone 45 mg + Metformin N=416
At least one congestive heart failure event | 0 | 1 (0.6%) |  | 0 | 1 (0.2%)
Hospitalized | 0 | 1 (0.6%) |  | 0 | 1 (0.2%)

Table 8: Treatment-Emergent Adverse Events of Congestive Heart Failure (CHF) in Patients with NYHA Class II or III Congestive Heart Failure Treated with Pioglitazone or Glyburide
 | Number (%) of Subjects
 | Pioglitazone N=262 | Glyburide N=256
Death due to cardiovascular causes (adjudicated) | 5 (1.9%) | 6 (2.3%)
Overnight hospitalization for worsening CHF (adjudicated) | 26 (9.9%) | 12 (4.7%)
Emergency room visit for CHF (adjudicated) | 4 (1.5%) | 3 (1.2%)
Patients experiencing CHF progression during study | 35 (13.4%) | 21 (8.2%)

Congestive heart failure events leading to hospitalization that occurred during the PROactive trial are summarized in Table 9.

Table 9: Treatment-Emergent Adverse Events of Congestive Heart Failure (CHF) in PROactive Trial
 | Number (%) of Patients
 | Placebo N=2,633 | Pioglitazone N=2,605
At least one hospitalized congestive heart failure event | 108 (4.1%) | 149 (5.7%)
Fatal | 22 (0.8%) | 25 (1.0%)
Hospitalized, nonfatal | 86 (3.3%) | 124 (4.7%)

Cardiovascular Safety

In the PROactive trial, 5,238 patients with type 2 diabetes mellitus and a history of macrovascular disease were randomized to pioglitazone (N=2,605), force-titrated up to 45 mg daily or placebo (N=2,633) in addition to standard of care. Almost all patients (95%) were receiving cardiovascular medications (beta blockers, ACE inhibitors, angiotensin II receptor blockers, calcium channel blockers, nitrates, diuretics, aspirin, statins, and fibrates). At baseline, patients had a mean age of 62 years, mean duration of diabetes of 9.5 years, and mean HbA1c of 8.1%. Mean duration of follow-up was 34.5 months.

The primary objective of this trial was to examine the effect of pioglitazone on mortality and macrovascular morbidity in patients with type 2 diabetes mellitus who were at high risk for macrovascular events. The primary efficacy variable was the time to the first occurrence of any event in a cardiovascular composite endpoint that included all-cause mortality, nonfatal myocardial infarction (MI) including silent MI, stroke, acute coronary syndrome, cardiac intervention including coronary artery bypass grafting or percutaneous intervention, major leg amputation above the ankle, and bypass surgery or revascularization in the leg. A total of 514 (19.7%) patients treated with pioglitazone and 572 (21.7%) placebo-treated patients experienced at least one event from the primary composite endpoint (HR = 0.90; 95% CI: 0.80, 1.02; p=0.10).

Although there was no statistically significant difference between pioglitazone and placebo for the three year incidence of a first event within this composite, there was no increase in mortality or in total macrovascular events with pioglitazone. The number of first occurrences and total individual events contributing to the primary composite endpoint is shown in Table 10.

Table 10: PROactive Trial: Number of First and Total Events for Each Component Within the Cardiovascular Composite Endpoint
Cardiovascular Events | Placebo N=2,633 |  | Pioglitazone N=2,605
Cardiovascular Events | First Events n (%) | Total events n | First Events n (%) | Total events n
Any event | 572 (21.7) | 900 | 514 (19.7) | 803
All-cause mortality | 122 (4.6) | 186 | 110 (4.2) | 177
Nonfatal myocardial infarction (MI) | 118 (4.5) | 157 | 105 (4.0) | 131
Stroke | 96 (3.6) | 119 | 76 (2.9) | 92
Acute coronary syndrome | 63 (2.4) | 78 | 42 (1.6) | 65
Cardiac intervention (CABG/PCI) | 101 (3.8) | 240 | 101 (3.9) | 195
Major leg amputation | 15 (0.6) | 28 | 9 (0.3) | 28
Leg revascularization | 57 (2.2) | 92 | 71 (2.7) | 115
CABG = coronary artery bypass grafting; PCI = percutaneous intervention.

Weight Gain

Dose-related weight gain occurs when pioglitazone is used alone or in combination with other antidiabetic medications. The mechanism of weight gain is unclear but probably involves a combination of fluid retention and fat accumulation.

Tables 11, 12, and 13 summarize the changes in body weight with pioglitazone and placebo in the 16 to 26 week randomized, double-blind monotherapy and 16 to 24 week combination add-on therapy trials, the PROactive trial, and the 24 week ACTOPLUS MET trial.

Table 11: Weight Changes (kg) from Baseline During Randomized, Double-Blind Clinical Trials
 |  | Control Group (Placebo) | Pioglitazone 15 mg | Pioglitazone 30 mg | Pioglitazone 45 mg
 |  | Median (25th, 75th percentile) | Median (25th, 75th percentile) | Median (25th, 75th percentile) | Median (25th, 75th percentile)
Monotherapy (16 to 26 weeks) |  | -1.4 (-2.7, 0.0) N=256 | 0.9 (-0.5, 3.4) N=79 | 1.0 (-0.9, 3.4) N=188 | 2.6 (0.2, 5.4) N=79
Combination Therapy (16 to 24 weeks) | Sulfonylurea | -0.5 (-1.8, 0.7) N=187 | 2.0 (0.2, 3.2) N=183 | 3.1 (1.1, 5.4) N=528 | 4.1 (1.8, 7.3) N=333
Combination Therapy (16 to 24 weeks) | Metformin | -1.4 (-3.2, 0.3) N=160 | N/A | 0.9 (-1.3, 3.2) N=567 | 1.8 (-0.9, 5.0) N=407
Combination Therapy (16 to 24 weeks) | Insulin | 0.2 (-1.4, 1.4) N=182 | 2.3 (0.5, 4.3) N=190 | 3.3 (0.9, 6.3) N=522 | 4.1 (1.4, 6.8) N=338

Table 12: Median Change in Body Weight in Patients Treated with Pioglitazone vs Patients Treated with Placebo During the Double-Blind Treatment Period in the PROactive Trial
 | Placebo | Pioglitazone
 | Median (25th, 75th percentile) | Median (25th, 75th percentile)
Change from baseline to final visit (kg) | -0.5 (-3.3, 2.0) N=2,581 | +3.6 (0.0, 7.5) N=2,560
Note: Median exposure for both pioglitazone and placebo was 2.7 years.

Table 13: Weight Changes (kg) from Baseline During Double-Blind Clinical Trial with ACTOPLUS MET in Patients with Inadequate Glycemic Control on Diet and Exercise
 | ACTOPLUS MET 15/850 mg Twice Daily | Pioglitazone 15 mg Twice Daily | Metformin 850 mg Twice Daily
 | Median (25th, 75th percentile) | Median (25th, 75th percentile) | Median (25th, 75th percentile)
Change from baseline to final visit (kg) | 1.00 (-1.0, 3.0) N=198 | 1.35 (-0.7, 4.1) N=178 | -1.00 (-2.6, 0.4) N=203
Note: Trial duration of 24 weeks.

Edema

Edema induced from taking pioglitazone is reversible when pioglitazone is discontinued. The edema usually does not require hospitalization unless there is co-existing congestive heart failure.

In the 24 week ACTOPLUS MET trial, edema was reported in 3.0% of patients in the ACTOPLUS MET group, 4.2% in the pioglitazone monotherapy group, and 1.4% in the metformin monotherapy group.

A summary of the frequency and types of edema adverse events occurring in clinical investigations of pioglitazone is provided in Table 14.

Table 14: Adverse Events of Edema in Patients Treated with Pioglitazone
 |  | Number (%) of Patients
 |  | Placebo | Pioglitazone 15 mg | Pioglitazone 30 mg | Pioglitazone 45 mg
Monotherapy (16 to 26 weeks) |  | 3 (1.2%) N=259 | 2 (2.5%) N= 81 | 13 (4.7%) N= 275 | 11 (6.5%) N=169
Combined Therapy (16 to 24 weeks) | Sulfonylurea | 4 (2.1%) N=187 | 3 (1.6%) N=184 | 61 (11.3%) N=540 | 81 (23.1%) N=351
Combined Therapy (16 to 24 weeks) | Metformin | 4 (2.5%) N=160 | N/A | 34 (5.9%) N=579 | 58 (13.9%) N=416
Combined Therapy (16 to 24 weeks) | Insulin | 13 (7.0%) N=187 | 24 (12.6%) N=191 | 109 (20.5%) N=533 | 90 (26.1%) N=345
Note: The preferred terms of edema peripheral, generalized edema, pitting edema, and fluid retention were combined to form the aggregate term of “edema.”

Table 15: Adverse Events of Edema in Patients in the PROactive Trial
Number (%) of Patients
Placebo N=2,633 | Pioglitazone N=2,605
419 (15.9%) | 712 (27.3%)
Note: The preferred terms of edema peripheral, generalized edema, pitting edema, and fluid retention were combined to form the aggregate term of “edema.”

Hepatic Effects

There has been no evidence of pioglitazone-induced hepatotoxicity in the pioglitazone controlled clinical trial database to date. One randomized, double-blind, three year trial comparing pioglitazone to glyburide as add-on to metformin and insulin therapy was specifically designed to evaluate the incidence of serum ALT elevation to greater than three times the upper limit of the reference range, measured every eight weeks for the first 48 weeks of the trial then every 12 weeks thereafter. A total of 3/1,051 (0.3%) patients treated with pioglitazone and 9/1,046 (0.9%) patients treated with glyburide developed ALT values greater than three times the upper limit of the reference range. None of the patients treated with pioglitazone in the pioglitazone controlled clinical trial database to date have had a serum ALT greater than three times the upper limit of the reference range and a corresponding total bilirubin greater than two times the upper limit of the reference range, a combination predictive of the potential for severe drug-induced liver injury.

Hypoglycemia

In the pioglitazone clinical trials, adverse events of hypoglycemia were reported based on clinical judgment of the investigators and did not require confirmation with fingerstick glucose testing.

In the 16 week add-on to sulfonylurea trial, the incidence of reported hypoglycemia was 3.7% with pioglitazone 30 mg and 0.5% with placebo. In the 16 week add-on to insulin trial, the incidence of reported hypoglycemia was 7.9% with pioglitazone 15 mg, 15.4% with pioglitazone 30 mg, and 4.8% with placebo.

The incidence of reported hypoglycemia was higher with pioglitazone 45 mg compared to pioglitazone 30 mg in both the 24 week add-on to sulfonylurea trial (15.7% vs 13.4%) and in the 24-week add-on to insulin trial (47.8% vs 43.5%).

Three patients in these four trials were hospitalized due to hypoglycemia. All three patients were receiving pioglitazone 30 mg (0.9%) in the 24 week add-on to insulin trial. An additional 14 patients reported severe hypoglycemia (defined as causing considerable interference with patient's usual activities) that did not require hospitalization. These patients were receiving pioglitazone 45 mg in combination with sulfonylurea (n=2) or pioglitazone 30 mg or 45 mg in combination with insulin (n=12).

Urinary Bladder Tumors

Tumors were observed in the urinary bladder of male rats in the two year carcinogenicity study [see Nonclinical Toxicology (13.1)]. During the three-year PROactive clinical trial, 14 patients out of 2,605 (0.54%) randomized to pioglitazone and 5 out of 2,633 (0.19%) randomized to placebo were diagnosed with bladder cancer. After excluding patients in whom exposure to study drug was less than one year at the time of diagnosis of bladder cancer, there were 6 (0.23%) cases on pioglitazone and 2 (0.08%) cases on placebo. After completion of the trial, a large subset of patients was observed for up to 10 additional years, with little additional exposure to pioglitazone. During the 13 years of both PROactive and observational follow-up, the occurrence of bladder cancer did not differ between patients randomized to pioglitazone or placebo (HR = 1.00; [95% CI: 0.59 1.72]) [see Warnings and Precautions (5.6)].

Metformin HCl

In a double-blind clinical study of metformin in patients with type 2 diabetes mellitus, a total of 141 patients received metformin therapy (up to 2,550 mg per day) and 145 patients received placebo. Adverse reactions reported in greater than 5% of the metformin patients, and that were more common in metformin than placebo-treated patients, are listed in Table 16. In this trial, diarrhea led to discontinuation of study medication in 6% of patients treated with metformin.

Table 16: Most Common Adverse Reactions (>5.0%) in a Placebo-Controlled Clinical Study of Metformin Monotherapy [Reactions that were more common in metformin than placebo-treated patients.]
Adverse Reaction | Metformin Monotherapy (n=141) | Placebo (n=145)
Adverse Reaction | % of Patients
Diarrhea | 53.2 | 11.7
Nausea/Vomiting | 25.5 | 8.3
Flatulence | 12.1 | 5.5
Asthenia | 9.2 | 5.5
Indigestion | 7.1 | 4.1
Abdominal Discomfort | 6.4 | 4.8
Headache | 5.7 | 4.8

Laboratory Abnormalities

Pioglitazone

Hematologic Effects

Pioglitazone may cause decreases in hemoglobin and hematocrit. In placebo-controlled monotherapy trials, mean hemoglobin values declined by 2% to 4% in patients treated with pioglitazone compared with a mean change in hemoglobin of -1% to +1% in placebo-treated patients. These changes primarily occurred within the first four to 12 weeks of therapy and remained relatively constant thereafter. These changes may be related to increased plasma volume associated with pioglitazone therapy and are not likely to be associated with any clinically significant hematologic effects.

Creatine Phosphokinase

During protocol-specified measurement of serum creatine phosphokinase (CPK) in pioglitazone clinical trials, an isolated elevation in CPK to greater than 10 times the upper limit of the reference range was noted in nine (0.2%) patients treated with pioglitazone (values of 2,150 to 11,400 IU/L) and in no comparator-treated patients. Six of these nine patients continued to receive pioglitazone, two patients were noted to have the CPK elevation on the last day of dosing, and one patient discontinued pioglitazone due to the elevation. These elevations resolved without any apparent clinical sequelae. The relationship of these events to pioglitazone therapy is unknown.

Metformin

Vitamin B12 Concentrations

In metformin clinical trials of 29-week duration, a decrease to subnormal levels of previously normal serum vitamin B12 levels was observed in approximately 7% of patients.

6.2 Postmarketing Experience

The following adverse reactions have been identified during post-approval use of pioglitazone and/or metformin. Because these reactions are reported voluntarily from a population of uncertain size, it is not always possible to reliably estimate their frequency or establish a causal relationship to drug exposure.

Pioglitazone

Cardiac Disorders: Rapid increases in weight, edema, congestive heart failure with and without previously known heart disease or concomitant insulin administration

Eye Disorders: New onset or worsening diabetic macular edema with decreased visual acuity

Hepatobiliary Disorders: Fatal and nonfatal hepatic failure

Metformin

Hepatobiliary Disorders: Cholestatic, hepatocellular, and mixed hepatocellular liver injury.

7 DRUG INTERACTIONS

7.1 Strong CYP2C8 Inhibitors

An inhibitor of CYP2C8 (e.g., gemfibrozil) significantly increases the exposure (area under the serum concentration-time curve or AUC) and half-life (t½) of pioglitazone. Therefore, the maximum recommended dosage of ACTOPLUS MET is 15 mg of pioglitazone and 850 mg of metformin HCl once daily if used in combination with gemfibrozil or other strong CYP2C8 inhibitors [see Dosage and Administration (2.3), Clinical Pharmacology (12.3)].

7.2 CYP2C8 Inducers

An inducer of CYP2C8 (e.g., rifampin) may significantly decrease the exposure (AUC) of pioglitazone. Therefore, if an inducer of CYP2C8 is started or stopped during treatment with ACTOPLUS MET, changes in diabetes treatment may be needed based on clinical response without exceeding the maximum recommended daily dosage of ACTOPLUS MET (45 mg of pioglitazone and 2,550 mg of metformin HCl) [see Clinical Pharmacology (12.3)].

7.3 Carbonic Anhydrase Inhibitors

Topiramate or other carbonic anhydrase inhibitors (e.g., zonisamide, acetazolamide or dichlorphenamide) frequently causes a decrease in serum bicarbonate and induce non-anion gap, hyperchloremic metabolic acidosis. Concomitant use of these drugs with ACTOPLUS MET may increase the risk for lactic acidosis. Consider more frequent monitoring of these patients.

7.4 Drugs that Reduce Metformin Clearance

Concomitant use of drugs that interfere with common renal tubular transport systems involved in the renal elimination of metformin (e.g., organic cationic transporter-2 [OCT2]/multidrug and toxin extrusion [MATE] inhibitors such as ranolazine, vandetanib, dolutegravir, and cimetidine) could increase systemic exposure to metformin and may increase the risk for lactic acidosis [see Clinical Pharmacology (12.3)]. Consider the benefits and risks of concomitant use.

7.5 Alcohol

Alcohol is known to potentiate the effect of metformin on lactate metabolism. Warn patients against excessive alcohol intake while receiving ACTOPLUS MET.

7.6 Insulin Secretagogues or Insulin

Coadministration of ACTOPLUS MET with an insulin secretagogue (e.g., sulfonylurea) or insulin may increase the risk of hypoglycemia. If hypoglycemia occurs in a patient coadministered ACTOPLUS MET and an insulin secretagogue (e.g., sulfonylurea), the dose of the insulin secretagogue should be reduced.

7.7 Drugs Affecting Glycemic Control

Certain drugs tend to produce hyperglycemia and may lead to loss of glycemic control. These drugs include the thiazides and other diuretics, corticosteroids, phenothiazines, thyroid products, estrogens, oral contraceptives, phenytoin, nicotinic acid, sympathomimetics, calcium channel blockers, and isoniazid. When such drugs are administered to a patient receiving ACTOPLUS MET, the patient should be closely observed for loss of blood glucose control. When such drugs are withdrawn from a patient receiving ACTOPLUS MET, the patient should be observed closely for hypoglycemia.

7.8 Topiramate

A decrease in the exposure of pioglitazone and its active metabolites were noted with concomitant administration of pioglitazone and topiramate [see Clinical Pharmacology (12.3)]. The clinical relevance of this decrease is unknown; however, when ACTOPLUS MET and topiramate are used concomitantly, monitor patients for adequate glycemic control.

8 USE IN SPECIFIC POPULATIONS

8.1 Pregnancy

Risk Summary

Limited data with ACTOPLUS MET or pioglitazone in pregnant women are not sufficient to determine a drug-associated risk for major birth defects or miscarriage. Published studies with metformin use during pregnancy have not reported a clear association with metformin and major birth defect or miscarriage risk (see Data). There are risks to the mother and fetus associated with poorly controlled diabetes in pregnancy [see Clinical Considerations].

In animal reproduction studies, no adverse developmental effects were observed when pioglitazone was administered to pregnant rats and rabbits during organogenesis at exposures up to 5 and 35 times the 45 mg clinical dose, respectively, based on body surface area. No adverse developmental effects were observed when metformin was administered to pregnant Sprague Dawley rats and rabbits during the period of organogenesis at doses up to 2 to 6 times, respectively, a 2,000 mg clinical dose, based on body surface area (see Data).

The estimated background risk of major birth defects is 6 to 10% in women with pre-gestational diabetes with a HbA1c >7 and has been reported to be as high as 20 to 25% in women with a HbA1c >10. The estimated background risk of miscarriage for the indicated population is unknown. In the US general population, the estimated background risk of major birth defects and miscarriage in clinically recognized pregnancies is 2 to 4% and 15 to 20%, respectively.

Clinical Considerations

Disease-Associated Maternal and/or Embryo/Fetal Risk

Poorly controlled diabetes in pregnancy increases the maternal risk for diabetic ketoacidosis, pre-eclampsia, spontaneous abortions, preterm delivery, still birth and delivery complications. Poorly controlled diabetes increases the fetal risk for major birth defects, still birth, and macrosomia related morbidity.

Data

Human Data

Published data from postmarketing studies have not reported a clear association with metformin and major birth defects, miscarriage, or adverse maternal or fetal outcomes when metformin was used during pregnancy. However, these studies cannot definitely establish the absence of any metformin-associated risk because of methodological limitations, including small sample size and inconsistent comparator groups.

Animal Data

Pioglitazone and Metformin HCl

Animal reproduction studies were not conducted with the combined products in ACTOPLUS MET. The following data are based on studies conducted with the individual components of ACTOPLUS MET.

Pioglitazone

Pioglitazone administered to pregnant rats during organogenesis did not cause adverse developmental effects at a dose of 20 mg/kg (~5 times the 45 mg clinical dose), but delayed parturition and reduced embryo-fetal viability at 40 and 80 mg/kg, or ≥9 times the 45 mg clinical dose, by body surface area. In pregnant rabbits administered pioglitazone during organogenesis, no adverse developmental effects were observed at 80 mg/kg (~35 times the 45 mg clinical dose), but reduced embryo-fetal viability at 160 mg/kg, or ~69 times the 45 mg clinical dose, by body surface area. When pregnant rats received pioglitazone during late gestation and lactation, delayed postnatal development, attributed to decreased body weight, occurred in offspring at maternal doses of 10 mg/kg and above or ≥2 times the 45 mg clinical dose, by body surface area.

Metformin HCl

Metformin HCl did not cause adverse developmental effects when administered to pregnant Sprague Dawley rats and rabbits up to 600 mg/kg/day during the period of organogenesis. This represents an exposure of about 2 to 6 times a 2,000 mg clinical dose based on body surface area (mg/m^2) for rats and rabbits, respectively.

8.2 Lactation

Risk Summary

There is no information regarding the presence of ACTOPLUS MET or pioglitazone in human milk, the effects on the breastfed infant, or the effects on milk production. Pioglitazone is present in rat milk; however, due to species-specific differences in lactation physiology, animal data may not reliably predict drug levels in human milk. Limited published studies report that metformin is present in human milk (see Data). However, there is insufficient information on the effects of metformin on the breastfed infant and no available information on the effects of metformin on milk production. The developmental and health benefits of breastfeeding should be considered along with the mother's clinical need for ACTOPLUS MET and any potential adverse effects on the breastfed infant from ACTOPLUS MET or from the underlying maternal condition.

Data

Published clinical lactation studies report that metformin is present in human milk which resulted in infant doses approximately 0.11% to 1% of the maternal weight-adjusted dosage and a milk/plasma ratio ranging between 0.13 and 1. However, the studies were not designed to definitely establish the risk of use of metformin during lactation because of small sample size and limited adverse event data collected in infants.

8.3 Females and Males of Reproductive Potential

Discuss the potential for unintended pregnancy with premenopausal women as therapy with ACTOPLUS MET, may result in ovulation in some anovulatory women.

8.4 Pediatric Use

Safety and effectiveness of ACTOPLUS MET in pediatric patients have not been established.

ACTOPLUS MET is not recommended for use in pediatric patients based on adverse effects observed in adults, including fluid retention and congestive heart failure, fractures, and urinary bladder tumors [see Warnings and Precautions (5.1, 5.3, 5.6, 5.7)].

8.5 Geriatric Use

Pioglitazone

A total of 92 patients (15.2%) treated with pioglitazone in the three pooled 16 to 26 week double-blind, placebo-controlled, monotherapy trials were ≥65 years old and two patients (0.3%) were ≥75 years old. In the two pooled 16 to 24 week add-on to sulfonylurea trials, 201 patients (18.7%) treated with pioglitazone were ≥65 years old and 19 (1.8%) were ≥75 years old. In the two pooled 16 to 24 week add-on to metformin trials, 155 patients (15.5%) treated with pioglitazone were ≥65 years old and 19 (1.9%) were ≥75 years old. In the two pooled 16 to 24 week add-on to insulin trials, 272 patients (25.4%) treated with pioglitazone were ≥65 years old and 22 (2.1%) were ≥75 years old.

In PROactive Trial, 1,068 patients (41.0%) treated with pioglitazone were ≥65 years old and 42 (1.6%) were ≥75 years old.

In pharmacokinetic studies with pioglitazone, no significant differences were observed in pharmacokinetic parameters between elderly and younger patients [see Clinical Pharmacology (12.3)].

Although clinical experiences have not identified differences in effectiveness and safety between the elderly (≥65 years) and younger patients, these conclusions are limited by small sample sizes for patients ≥75 years old.

Metformin HCl

Controlled clinical studies of metformin did not include sufficient numbers of elderly patients to determine whether they respond differently from younger patients, although other reported clinical experience has not identified differences in responses between the elderly and young patients. In general, dose selection for an elderly patient should be cautious, usually starting at the low end of the dosing range, reflecting the greater frequency of decreased hepatic, renal, or cardiac function, and of concomitant disease or other drug therapy and the higher risk of lactic acidosis. Assess renal function more frequently in elderly patients [see Warnings and Precautions (5.2), Dosage and Administration (2.2)].

8.6 Renal Impairment

Metformin is substantially excreted by the kidney, and the risk of metformin accumulation and lactic acidosis increases with the degree of renal impairment. ACTOPLUS MET is contraindicated in severe renal impairment, which includes patients with an eGFR below 30 mL/min [see Dosage and Administration (2.2), Contraindications (4), Warnings and Precautions (5.2), Clinical Pharmacology (12.3)].

8.7 Hepatic Impairment

Use of metformin in patients with hepatic impairment has been associated with some cases of lactic acidosis. ACTOPLUS MET is not recommended in patients with hepatic impairment [see Warnings and Precautions (5.2)].

10 OVERDOSAGE

Pioglitazone

During controlled clinical trials, one case of overdose with pioglitazone was reported. A male patient took 120 mg per day for four days, then 180 mg per day for seven days. The patient denied any clinical symptoms during this period.

Metformin HCl

Overdose of metformin HCl has occurred, including ingestion of amounts greater than 50 grams. Hypoglycemia was reported in approximately 10% of cases, but no causal association with metformin HCl has been established. Lactic acidosis has been reported in approximately 32% of metformin overdose cases [see Warnings and Precautions (5.2)]. Metformin is dialyzable with a clearance of up to 170 mL/min under good hemodynamic conditions. Therefore, hemodialysis may be useful for removal of accumulated metformin from patients in whom metformin overdosage is suspected.

In the event of overdosage, contact the Poison Help Line (1-800-222-1222) or a medical toxicologist for additional overdosage management recommendations. Appropriate supportive treatment should be initiated according to the patient’s clinical signs and symptoms.

11 DESCRIPTION

ACTOPLUS MET tablets are a thiazolidinediones and biguanide combination product that contains two oral antidiabetic medications: pioglitazone HCl and metformin HCl.

Pioglitazone [(±)-5-[[4-[2-(5-ethyl-2-pyridinyl) ethoxy]phenyl]methyl]-2,4-] thiazolidinedione monohydrochloride contains one asymmetric carbon, and the compound is synthesized and used as the racemic mixture. The two enantiomers of pioglitazone interconvert in vivo. No differences were found in the pharmacologic activity between the two enantiomers. The structural formula is as shown:

pioglitazone HCl

Pioglitazone HCl is an odorless white crystalline powder that has a molecular formula of C19H20N2O3S•HCl and a molecular weight of 392.90 daltons. It is soluble in N,N-dimethylformamide, slightly soluble in anhydrous ethanol, very slightly soluble in acetone and acetonitrile, practically insoluble in water, and insoluble in ether.

Metformin HCl (N,N-dimethylimidodicarbonimidic diamide HCl) is a white crystalline powder with a molecular formula of C4H11N5•HCl and a molecular weight of 165.62. Metformin HCl is freely soluble in water and is practically insoluble in acetone, ether, and chloroform. The pKa of metformin is 12.4. The pH of a 1% aqueous solution of metformin HCl is 6.68. The structural formula is as shown:

metformin HCl

ACTOPLUS MET is available as a tablet for oral administration containing 15 mg pioglitazone (as the base) with 850 mg metformin HCl (15 mg/850 mg) formulated with the following excipients: povidone USP, microcrystalline cellulose NF, croscarmellose sodium NF, magnesium stearate NF, hypromellose 2910 USP, polyethylene glycol 8000 NF, titanium dioxide USP, and talc USP.

12 CLINICAL PHARMACOLOGY

12.1 Mechanism of Action

ACTOPLUS MET combines two antihyperglycemic agents: pioglitazone and metformin.

Pioglitazone

Pioglitazone is a thiazolidinedione that depends on the presence of insulin for its mechanism of action. Pioglitazone decreases insulin resistance in the periphery and in the liver resulting in increased insulin-dependent glucose disposal and decreased hepatic glucose output. Pioglitazone is not an insulin secretagogue. Pioglitazone is an agonist for peroxisome proliferator-activated receptor-gamma (PPARγ). PPAR receptors are found in tissues important for insulin action such as adipose tissue, skeletal muscle, and liver. Activation of PPARγ nuclear receptors modulates the transcription of a number of insulin responsive genes involved in the control of glucose and lipid metabolism.

In animal models of diabetes, pioglitazone reduces the hyperglycemia, hyperinsulinemia, and hypertriglyceridemia characteristic of insulin-resistant states such as type 2 diabetes mellitus. The metabolic changes produced by pioglitazone result in increased responsiveness of insulin-dependent tissues and are observed in numerous animal models of insulin resistance.

Because pioglitazone enhances the effects of circulating insulin (by decreasing insulin resistance), it does not lower blood glucose in animal models that lack endogenous insulin.

Metformin HCl

Metformin HCl improves glucose tolerance in patients with type 2 diabetes mellitus, lowering both basal and postprandial plasma glucose. Metformin decreases hepatic glucose production, decreases intestinal absorption of glucose, and improves insulin sensitivity by increasing peripheral glucose uptake and utilization. Metformin does not produce hypoglycemia in either patients with type 2 diabetes mellitus or healthy subjects [except in specific circumstances, see Warnings and Precautions (5.4)] and does not cause hyperinsulinemia. With metformin therapy, insulin secretion remains unchanged while fasting insulin levels and day-long plasma insulin response may actually decrease.

12.2 Pharmacodynamics

Pioglitazone

Clinical studies demonstrate that pioglitazone improves insulin sensitivity in insulin-resistant patients. Pioglitazone enhances cellular responsiveness to insulin, increases insulin-dependent glucose disposal and improves hepatic sensitivity to insulin. In patients with type 2 diabetes mellitus, the decreased insulin resistance produced by pioglitazone results in lower plasma glucose concentrations, lower plasma insulin concentrations, and lower HbA1c values. In controlled clinical trials, pioglitazone had an additive effect on glycemic control when used in combination with a sulfonylurea, metformin, or insulin [see Clinical Studies (14)].

Patients with lipid abnormalities were included in clinical trials with pioglitazone. Overall, patients treated with pioglitazone had mean decreases in serum triglycerides, mean increases in HDL cholesterol, and no consistent mean changes in LDL and total cholesterol. There is no conclusive evidence of macrovascular benefit with pioglitazone [see Adverse Reactions (6.1)].

In a 26 week, placebo-controlled, dose-ranging monotherapy study, mean serum triglycerides decreased in the 15 mg, 30 mg, and 45 mg pioglitazone dose groups compared to a mean increase in the placebo group. Mean HDL cholesterol increased to a greater extent in patients treated with pioglitazone than in the placebo-treated patients. There were no consistent differences for LDL and total cholesterol in patients treated with pioglitazone compared to placebo (see Table 17).

Table 17: Lipids in a 26 Week Placebo-Controlled Monotherapy Dose-Ranging Study
 | Placebo | Pioglitazone 15 mg Once Daily | Pioglitazone 30 mg Once Daily | Pioglitazone 45 mg Once Daily
Triglycerides (mg/dL) | N=79 | N=79 | N=84 | N=77
Baseline (mean) | 263 | 284 | 261 | 260
Percent change from baseline (adjusted mean [Adjusted for baseline, pooled center, and pooled center by treatment interaction.]) | 4.8% | -9.0% [p<0.05 vs placebo.] | -9.6% | -9.3%
HDL Cholesterol (mg/dL) | N=79 | N=79 | N=83 | N=77
Baseline (mean) | 42 | 40 | 41 | 41
Percent change from baseline (adjusted mean) | 8.1% | 14.1% | 12.2% | 19.1%
LDL Cholesterol (mg/dL) | N=65 | N=63 | N=74 | N=62
Baseline (mean) | 139 | 132 | 136 | 127
Percent change from baseline (adjusted mean) | 4.8% | 7.2% | 5.2% | 6.0%
Total Cholesterol (mg/dL) | N=79 | N=79 | N=84 | N=77
Baseline (mean) | 225 | 220 | 223 | 214
Percent change from baseline (adjusted mean) | 4.4% | 4.6% | 3.3% | 6.4%

In the two other monotherapy studies (16 weeks and 24 weeks) and in combination therapy studies with metformin (16 weeks and 24 weeks), the results were generally consistent with the data above.

12.3 Pharmacokinetics

Absorption

ACTOPLUS MET

In bioequivalence studies of ACTOPLUS MET 15 mg/500 mg and 15 mg/850 mg, the area under the curve (AUC) and maximum concentration (Cmax) of both the pioglitazone and the metformin component following a single dose of the combination tablet were bioequivalent to ACTOS® 15 mg concomitantly administered with metformin HCl immediate release (500 mg or 850 mg, respectively) tablets under fasted conditions in healthy subjects.

Administration of ACTOPLUS MET 15 mg/850 mg with food resulted in no change in overall exposure of pioglitazone. With metformin there was no change in AUC; however, mean peak serum concentration of metformin was decreased by 28% when administered with food. A delayed time to peak serum concentration was observed for both components (1.9 hours for pioglitazone and 0.8 hours for metformin) under fed conditions. These changes are not likely to be clinically significant.

Pioglitazone

Following once-daily administration of pioglitazone, steady-state serum concentrations of both pioglitazone and its major active metabolites, M-III (keto derivative of pioglitazone) and M-IV (hydroxyl derivative of pioglitazone), are achieved within seven days. At steady state, M-III and M-IV reach serum concentrations equal to or greater than that of pioglitazone. At steady state, in both healthy volunteers and patients with type 2 diabetes mellitus, pioglitazone comprises approximately 30 to 50% of the peak total pioglitazone serum concentrations (pioglitazone plus active metabolites) and 20 to 25% of the total AUC.

Cmax, AUC, and trough serum concentrations (Cmin) for pioglitazone and M-III and M-IV, increased proportionally with administered doses of 15 mg and 30 mg per day.

Following oral administration of pioglitazone, Tmax of pioglitazone was within two hours. Food delays the Tmax to three to four hours, but does not alter the extent of absorption (AUC).

Metformin HCl

The absolute bioavailability of a 500 mg metformin tablet given under fasting conditions is approximately 50 to 60%. Studies using single oral doses of metformin tablets of 500 mg to 1500 mg, and 850 mg to 2,550 mg, indicate that there is a lack of dose proportionality with increasing doses, which is due to decreased absorption rather than an alteration in elimination. At usual clinical doses and dosing schedules of metformin, steady-state plasma concentrations of metformin are reached within 24 to 48 hours and are generally <1 mcg/mL. During controlled clinical trials, maximum metformin plasma levels did not exceed 5 mcg/mL, even at maximum doses.

Food decreases the rate and extent of metformin absorption, as shown by a 40% lower mean Cmax, a 25% lower AUC, and a 35 minute prolongation of Tmax following administration of a single 850 mg tablet of metformin with food, compared to the same tablet strength administered fasting. The clinical relevance of these decreases is unknown.

Distribution

Pioglitazone

The mean apparent volume of distribution (Vd/F) of pioglitazone following single-dose administration is 0.63 ± 0.41 (mean ± SD) L/kg of body weight. Pioglitazone is extensively protein bound (>99%) in human serum, principally to serum albumin. Pioglitazone also binds to other serum proteins, but with lower affinity. M-III and M-IV are also extensively bound (>98%) to serum albumin.

Metformin HCl

The Vd/F of metformin following single oral doses of 850 mg immediate-release metformin averaged 654 ± 358 L. Metformin is negligibly bound to plasma proteins. Metformin partitions into erythrocytes, most likely as a function of time.

Elimination

Metabolism

Pioglitazone

Pioglitazone is extensively metabolized by hydroxylation and oxidation; the metabolites also partly convert to glucuronide or sulfate conjugates. Metabolites M-III and M-IV are the major circulating active metabolites in humans.

In vitro data demonstrate that multiple CYP isoforms are involved in the metabolism of pioglitazone which include CYP2C8 and, to a lesser degree, CYP3A4 with additional contributions from a variety of other isoforms, including the mainly extrahepatic CYP1A1. In vivo study of pioglitazone in combination with gemfibrozil, a strong CYP2C8 inhibitor, showed that pioglitazone is a CYP2C8 substrate [see Dosage and Administration (2.3), Drug Interactions (7.1)]. Urinary 6ß-hydroxycortisol/cortisol ratios measured in patients treated with pioglitazone showed that pioglitazone is not a strong CYP3A4 enzyme inducer.

Metformin HCl

Intravenous single-dose studies in healthy subjects demonstrate that metformin is excreted unchanged in the urine and does not undergo hepatic metabolism (no metabolites have been identified in humans) nor biliary excretion.

Excretion

Pioglitazone

Following oral administration, approximately 15 to 30% of the pioglitazone dose is recovered in the urine. Renal elimination of pioglitazone is negligible and the drug is excreted primarily as metabolites and their conjugates. It is presumed that most of the oral dose is excreted into the bile either unchanged or as metabolites and eliminated in the feces.

The mean serum half-life (t½) of pioglitazone and its metabolites (M-III and M-IV) range from three to seven hours and 16 to 24 hours, respectively. Pioglitazone has an apparent clearance, CL/F, calculated to be five to seven L/hr.

Metformin HCl

Renal clearance is approximately 3.5 times greater than creatinine clearance (CrCl), which indicates that tubular secretion is the major route of metformin elimination. Following oral administration, approximately 90% of the absorbed drug is eliminated via the renal route within the first 24 hours, with a plasma elimination t½ of approximately 6.2 hours. In blood, the elimination t½ is approximately 17.6 hours, suggesting that the erythrocyte mass may be a compartment of distribution.

Specific Populations

Geriatric Patients

Pioglitazone

In healthy elderly subjects, Cmax of pioglitazone was not significantly different, but AUC values were approximately 21% higher than those achieved in younger subjects. The mean t½ of pioglitazone was also prolonged in elderly subjects (about ten hours) as compared to younger subjects (about seven hours). These changes are not considered clinically relevant.

Metformin HCl

Limited data from controlled pharmacokinetic studies of metformin in healthy elderly subjects suggest that total CL/F is decreased, the t½ is prolonged, and Cmax is increased, compared to healthy young subjects. From these data, it appears that the change in metformin pharmacokinetics with aging is primarily accounted for by a change in renal function.

Pediatric Patients

Pioglitazone

Safety and efficacy of pioglitazone in pediatric patients have not been established. ACTOPLUS MET is not recommended for use in pediatric patients [see Use in Specific Populations (8.4)].

Metformin HCl

After administration of a single oral metformin 500 mg tablet with food, geometric mean metformin Cmax and AUC differed less than 5% between pediatric type 2 diabetic patients (12 to 16 years of age) and gender- and weight-matched healthy adults (20 to 45 years of age), and all with normal renal function.

Male and Female Patients

Pioglitazone

The mean Cmax and AUC values of pioglitazone were increased 20 to 60% in females compared to males. In controlled clinical trials, HbA1c decreases from baseline were generally greater for females than for males (average mean difference in HbA1c 0.5%). Because therapy should be individualized for each patient to achieve glycemic control, no dosage adjustment is recommended based on gender alone.

Metformin HCl

Metformin pharmacokinetic parameters did not differ significantly between normal subjects and patients with type 2 diabetes mellitus when analyzed according to gender (males=19, females=16). Similarly, in controlled clinical studies in patients with type 2 diabetes mellitus, the antihyperglycemic effect of metformin was comparable in males and females.

Racial or Ethnic Groups

Pioglitazone

Pharmacokinetic data among various ethnic groups are not available.

Metformin HCl

No studies of metformin pharmacokinetic parameters according to race have been performed. In controlled clinical studies of metformin in patients with type 2 diabetes mellitus, the antihyperglycemic effect was comparable in Whites (n=249), Blacks or African Americans (n=51), and Hispanics or Latinos (n=24).

Patients with Renal Impairment

Pioglitazone

The serum elimination half-life of pioglitazone, M-III and M-IV remains unchanged in patients with moderate (CrCl 30 to 50 mL/min) and severe (CrCl <30 mL/min) renal impairment when compared to subjects with normal renal function. Therefore, no dosage adjustment in patients with renal impairment is required.

Metformin HCl

In patients with decreased renal function, the plasma and blood t1/2 of metformin is prolonged and the renal clearance is decreased [see Dosage and Administration (2.3), Contraindications (4), Warnings and Precautions (5.2)].

Patients with Hepatic Impairment

Pioglitazone

Compared with healthy controls, subjects with impaired hepatic function (Child-Turcotte-Pugh Grade B/C) have an approximate 45% reduction in pioglitazone and total pioglitazone (pioglitazone, M-III, and M-IV) mean Cmax but no change in the mean AUC values. Therefore, no dosage adjustment in patients with hepatic impairment is required.

There are postmarketing reports of liver failure with pioglitazone and clinical trials have generally excluded patients with serum ALT >2.5 times the upper limit of the reference range. Use ACTOPLUS MET with caution in patients with liver disease [see Warnings and Precautions (5.5)].

Metformin HCl

No pharmacokinetic studies of metformin have been conducted in subjects with hepatic impairment [see Warnings and Precautions (5.5)].

Drug Interaction Studies

Specific pharmacokinetic drug interaction studies with ACTOPLUS MET have not been performed, although such studies have been conducted with the individual pioglitazone and metformin components.

Pioglitazone

Table 18: Effect of Pioglitazone Coadministration on Systemic Exposure of Other Drugs
 | Coadministered Drug
Pioglitazone Dosage Regimen (mg) [Daily for 7 days unless otherwise noted.] | Name and Dose Regimens | Change in AUC [% change (with/without coadministered drug and no change = 0%); symbols of ↑ and ↓ indicate the exposure increase and decrease, respectively.] |  | Change in Cmax
45 mg (N = 12) | Warfarin [Pioglitazone had no clinically significant effect on prothrombin time.]
45 mg (N = 12) | Daily loading then maintenance doses based PT and INR values Quick's Value = 35 ± 5% | R-Warfarin | ↓3% | R-Warfarin | ↓2%
45 mg (N = 12) | Daily loading then maintenance doses based PT and INR values Quick's Value = 35 ± 5% | S-Warfarin | ↓1% | S-Warfarin | ↑1%
45 mg (N = 12) | Digoxin
45 mg (N = 12) | 0.200 mg twice daily (loading dose) then 0.250 mg daily (maintenance dose, 7 days) | ↑15% |  | ↑17%
45 mg daily for 21 days (N = 35) | Oral Contraceptive
45 mg daily for 21 days (N = 35) | [Ethinyl Estradiol (EE) 0.035 mg plus Norethindrone (NE) 1 mg] for 21 days | EE | ↓11% | EE | ↓13%
45 mg daily for 21 days (N = 35) | [Ethinyl Estradiol (EE) 0.035 mg plus Norethindrone (NE) 1 mg] for 21 days | NE | ↑3% | NE | ↓7%
45 mg (N = 23) | Fexofenadine
45 mg (N = 23) | 60 mg twice daily for 7 days | ↑30% |  | ↑37%
45 mg (N = 14) | Glipizide
45 mg (N = 14) | 5 mg daily for 7 days | ↓3% |  | ↓8%
45 mg daily for 8 days (N = 16) | Metformin
45 mg daily for 8 days (N = 16) | 1,000 mg single dose on Day 8 | ↓3% |  | ↓5%
45 mg (N = 21) | Midazolam
45 mg (N = 21) | 7.5 mg single dose on Day 15 | ↓26% |  | ↓26%
45 mg (N = 24) | Ranitidine
45 mg (N = 24) | 150 mg twice daily for 7 days | ↑1% |  | ↓1%
45 mg daily for 4 days (N = 24) | Nifedipine ER
45 mg daily for 4 days (N = 24) | 30 mg daily for 4 days | ↓13% |  | ↓17%
45 mg (N = 25) | Atorvastatin Calcium
45 mg (N = 25) | 80 mg daily for 7 days | ↓14% |  | ↓23%
45 mg (N = 22) | Theophylline
45 mg (N = 22) | 400 mg twice daily for 7 days | ↑2% |  | ↑5%

Table 19: Effect of Coadministered Drugs on Pioglitazone Systemic Exposure
Coadministered Drug and Dosage Regimen | Pioglitazone
Coadministered Drug and Dosage Regimen | Dose Regimen (mg) [Daily for 7 days unless otherwise noted.] | Change in AUC [Mean ratio (with/without coadministered drug and no change = 1-fold) % change (with/without coadministered drug and no change = 0%); symbols of ↑ and ↓ indicate the exposure increase and decrease, respectively.] | Change in Cmax
Gemfibrozil 600 mg twice daily for 2 days (N = 12) | 15 mg single dose | ↑3.2-fold [The half-life of pioglitazone increased from 8.3 hours to 22.7 hours in the presence of gemfibrozil [see Dosage and Administration (2.3), Drug Interactions (7.1)].] | ↑6%
Ketoconazole 200 mg twice daily for 7 days (N = 28) | 45 mg | ↑34% | ↑14%
Rifampin 600 mg daily for 5 days (N = 10) | 30 mg single dose | ↓54% | ↓5%
Fexofenadine 60 mg twice daily for 7 days (N = 23) | 45 mg | ↑1% | 0%
Ranitidine 150 mg twice daily for 4 days (N = 23) | 45 mg | ↓13% | ↓16%
Nifedipine ER 30 mg daily for 7 days (N = 23) | 45 mg | ↑5% | ↑4%
Atorvastatin Calcium 80 mg daily for 7 days (N = 24) | 45 mg | ↓24% | ↓31%
Theophylline 400 mg twice daily for 7 days (N = 22) | 45 mg | ↓4% | ↓2%
Topiramate 96 mg twice daily for 7 days [Indicates duration of concomitant administration with highest twice-daily dose of topiramate from Day 14 onwards over the 22 days of study.] | 30 mg | ↓15% [Additional decrease in active metabolites; 60% for M-III and 16% for M-IV.] | 0%
(N = 26)

Metformin HCl

Table 20: Effect of Coadministered Drug on Plasma Metformin Systemic Exposure
Coadministered Drug | Dose of Coadministered Drug [All metformin and coadministered drugs were given as single doses.] | Dose of Metformin | Geometric Mean Ratio (ratio with/without coadministered drug) No effect = 1.00
Coadministered Drug | Dose of Coadministered Drug [All metformin and coadministered drugs were given as single doses.] | Dose of Metformin | AUC [AUC = AUC0–∞.] | Cmax
No dosing adjustments required for the following:
Glyburide | 5 mg | 500 mg [Metformin HCl extended-release tablets, 500 mg.] | 0.98 [Ratio of arithmetic means.] | 0.99
Furosemide | 40 mg | 850 mg | 1.09 | 1.22
Nifedipine | 10 mg | 850 mg | 1.16 | 1.21
Propranolol | 40 mg | 850 mg | 0.90 | 0.94
Ibuprofen | 400 mg | 850 mg | 1.05 | 1.07
Drugs that are eliminated by renal tubular secretion may increase the accumulation of metformin [see Warnings and Precautions (5), Drug Interactions (7)].
Cimetidine | 400 mg | 850 mg | 1.40 | 1.61
Carbonic anhydrase inhibitors may cause metabolic acidosis [see Warnings and Precautions (5), Drug Interactions (7)].
Topiramate | 100 mg [At steady state with topiramate 100 mg every 12 hours and metformin 500 mg every 12 hours; AUC = AUC0-12h] | 500 mg | 1.25 | 1.17

Table 21: Effect of Metformin on Coadministered Drug Systemic Exposure
Coadministered Drug | Dose of Coadministered Drug [All metformin and coadministered drugs were given as single doses.] | Dose of Metformin | Geometric Mean Ratio (ratio with/without coadministered drug) No effect = 1.00
Coadministered Drug | Dose of Coadministered Drug [All metformin and coadministered drugs were given as single doses.] | Dose of Metformin | AUC [AUC = AUC0–∞.] | Cmax
No dosing adjustments required for the following:
Glyburide | 5 mg | 500 mg [AUC0-24 hr reported.] | 0.78 [Ratio of arithmetic means, p-value of difference <0.05.] | 0.63
Furosemide | 40 mg | 850 mg | 0.87 | 0.69
Nifedipine | 10 mg | 850 mg | 1.10 | 1.08
Propranolol | 40 mg | 850 mg | 1.01 | 0.94
Ibuprofen | 400 mg | 850 mg | 0.97 [Ratio of arithmetic means.] | 1.01
Cimetidine | 400 mg | 850 mg | 0.95 | 1.01

13 NONCLINICAL TOXICOLOGY

13.1 Carcinogenesis, Mutagenesis, Impairment of Fertility

ACTOPLUS MET

No animal studies have been conducted with ACTOPLUS MET. The following data are based on findings in studies performed with pioglitazone or metformin individually.

Pioglitazone

A two year carcinogenicity study was conducted in male and female rats at oral doses up to 63 mg/kg (approximately 14 times the maximum recommended human oral dose of 45 mg based on mg/m^2). Drug-induced tumors were not observed in any organ except for the urinary bladder of male rats. Benign and/or malignant transitional cell neoplasms were observed in male rats at 4 mg/kg/day and above (approximately equal to the maximum recommended human oral dose based on mg/m^2). Urinary calculi with subsequent irritation and hyperplasia were postulated as the mechanism for bladder tumors observed in male rats. A two year mechanistic study in male rats utilizing dietary acidification to reduce calculi formation was completed in 2009. Dietary acidification decreased but did not abolish the hyperplastic changes in the bladder. The presence of calculi exacerbated the hyperplastic response to pioglitazone but was not considered the primary cause of the hyperplastic changes.

The relevance to humans of the bladder findings in the male rat cannot be excluded.

A two year carcinogenicity study was also conducted in male and female mice at oral doses up to 100 mg/kg/day (approximately 11 times the maximum recommended human oral dose based on mg/m^2). No drug-induced tumors were observed in any organ.

Pioglitazone HCl was not mutagenic in a battery of genetic toxicology studies, including the Ames bacterial assay, a mammalian cell forward gene mutation assay (CHO/HPRT and AS52/XPRT), an in vitro cytogenetics assay using CHL cells, an unscheduled DNA synthesis assay, and an in vivo micronucleus assay.

No adverse effects upon fertility were observed in male and female rats at oral doses up to 40 mg/kg pioglitazone HCl daily prior to and throughout mating and gestation (approximately nine times the maximum recommended human oral dose based on mg/m^2).

Metformin HCl

Long-term carcinogenicity studies have been performed in rats (dosing duration of 104 weeks) and mice (dosing duration of 91 weeks) at doses up to and including 900 mg/kg/day and 1500 mg/kg/day, respectively. These doses are both approximately four times a human daily dose of 2000 mg of the metformin component of ACTOPLUS MET based on body surface area comparisons. No evidence of carcinogenicity with metformin was found in either male or female mice. Similarly, there was no tumorigenic potential observed with metformin in male rats. There was, however, an increased incidence of benign stromal uterine polyps in female rats treated with 900 mg/kg/day.

There was no evidence of mutagenic potential of metformin in the following in vitro tests: Ames test (S. typhimurium), gene mutation test (mouse lymphoma cells), or chromosomal aberrations test (human lymphocytes). Results in the in vivo mouse micronucleus test were also negative.

Fertility of male or female rats was unaffected by metformin when administered at doses as high as 600 mg/kg/day, which is approximately three times the maximum recommended human daily dose of the metformin component of ACTOPLUS MET based on body surface area comparisons.

13.2 Animal Toxicology and/or Pharmacology

Heart enlargement has been observed in mice (100 mg/kg), rats (4 mg/kg and above) and dogs (3 mg/kg) treated orally with pioglitazone HCl (approximately 11, one, and two times the maximum recommended human oral dose for mice, rats, and dogs, respectively, based on mg/m^2). In a one year rat study, drug-related early death due to apparent heart dysfunction occurred at an oral dose of 160 mg/kg/day (approximately 35 times the maximum recommended human oral dose based on mg/m^2). Heart enlargement was seen in a 13 week study in monkeys at oral doses of 8.9 mg/kg and above (approximately four times the maximum recommended human oral dose based on mg/m^2), but not in a 52 week study at oral doses up to 32 mg/kg (approximately 13 times the maximum recommended human oral dose based on mg/m^2).

14 CLINICAL STUDIES

14.1 Patients Who Have Inadequate Glycemic Control with Diet and Exercise Alone

In a 24 week, randomized, double-blind clinical trial, 600 patients with type 2 diabetes mellitus inadequately controlled with diet and exercise alone (mean baseline HbA1c 8.7%) were randomized to ACTOPLUS MET 15/850 mg, pioglitazone 15 mg, or metformin 850 mg twice daily. Statistically significant improvements in HbA1c and fasting plasma glucose (FPG) were observed in patients treated with ACTOPLUS MET compared to either pioglitazone or metformin alone (see Table 22).

Table 22: Glycemic Parameters in 24 Week Study of ACTOPLUS MET in Patients with Type 2 Diabetes Mellitus Inadequately Controlled with Diet and Exercise
Parameter | Treatment Group
Parameter | ACTOPLUS MET 15/850 mg Twice Daily | Pioglitazone 15 mg Twice Daily | Metformin 850 mg Twice Daily
HbA1c (%) | N=188 | N=162 | N=193
Baseline (mean) | 8.9 | 8.7 | 8.7
Change from Baseline (adjusted mean [Adjusted for baseline.]) | -1.8 | -1.0 | -1.0
Difference between ACTOPLUS MET (adjusted mean) 95% Confidence Interval |  | 0.9 [p ≤0.05 vs ACTOPLUS MET.] (0.5, 1.2) | 0.8 (0.5, 1.2)
% of patients with HbA1c ≤7% | 64 | 47 | 39
Fasting Plasma Glucose (mg/dL) | N=196 | N=176 | N=202
Baseline (mean) | 177 | 171 | 171
Change from Baseline (adjusted mean) | -40 | -22 | -25
Difference between ACTOPLUS MET (adjusted mean) 95% Confidence Interval |  | 18 (8, 28) | 15 (6, 25)

14.2 Patients Previously Treated with Metformin

The efficacy and safety of pioglitazone as add-on to metformin therapy have been established in two clinical studies [see Clinical Pharmacology (12.3)].

The two clinical trials testing pioglitazone as add-on to metformin therapy included patients with type 2 diabetes mellitus on any dose of metformin, either alone or in combination with another antidiabetic agent. All other antidiabetic agents were withdrawn at least three weeks prior to starting study treatment.

In the first trial, 328 patients were randomized to receive either 30 mg of pioglitazone or placebo once daily for 16 weeks in addition to their current metformin regimen. Treatment with pioglitazone as add-on to metformin produced statistically significant improvements in HbA1c and FPG at endpoint compared to placebo add-on to metformin (see Table 23).

Table 23: Glycemic Parameters in a 16 Week Placebo-Controlled, Add-on to Metformin Trial
 | Placebo + Metformin | Pioglitazone 30 mg + Metformin
Total Population
HbA1c (%) | N=153 | N=161
Baseline (mean) | 9.8 | 9.9
Change from baseline (adjusted mean [Adjusted for baseline, pooled center, and pooled center by treatment interaction.]) | 0.2 | -0.6
Difference from placebo + metformin (adjusted mean) 95% Confidence Interval |  | -0.8 [p ≤0.05 vs placebo + metformin.] (-1.2, -0.5)
Fasting Plasma Glucose (mg/dL) | N=157 | N=165
Baseline (mean) | 260 | 254
Change from baseline (adjusted mean) | -5 | -43
Difference from placebo + metformin (adjusted mean) 95% Confidence Interval |  | -38 (-49, -26)

In the second trial, 827 patients were randomized to receive either 30 mg or 45 mg of pioglitazone once daily for 24 weeks in addition to their current metformin regimen. The mean reduction from baseline at Week 24 in HbA1c was 0.8% for the 30 mg dose and 1.0% for the 45 mg dose (see Table 24). The mean reduction from baseline at Week 24 in FPG was 38 mg/dL for the 30 mg dose and 51 mg/dL for the 45 mg dose.

Table 24: Glycemic Parameters in a 24 Week Add-on to Metformin Study
 | Pioglitazone 30 mg + Metformin | Pioglitazone 45 mg + Metformin
Total Population
HbA1c (%) | N=400 | N=398
Baseline (mean) | 9.9 | 9.8
Change from baseline (adjusted mean [Adjusted for baseline, pooled center, and pooled center by treatment interaction.]) | -0.8 | -1.0
Difference from 30 mg daily pioglitazone + metformin (adjusted mean) (95% CI) |  | -0.2 (-0.5, 0.1)
Fasting Plasma Glucose (mg/dL) | N=398 | N=399
Baseline (mean) | 233 | 232
Change from baseline (adjusted mean) | -38 | -51
Difference from 30 mg daily pioglitazone + metformin (adjusted mean) (95% CI) |  | -12 [p ≤0.05 vs. 30 mg daily pioglitazone + metformin.] (-21, -4)
95% CI = 95% confidence interval.

The therapeutic effect of pioglitazone in combination with metformin was observed in patients regardless of the metformin dose.

16 HOW SUPPLIED/STORAGE AND HANDLING

ACTOPLUS MET is available in 15 mg pioglitazone (as the base)/850 mg metformin HCl tablets as follows:

15 mg/850 mg tablet: white to off-white, oblong, film-coated tablet with "4833M" on one side and "15/850" on the other, available in:

Bottles of 60 NDC 64764-158-60

Bottles of 180 NDC 64764-158-18

Storage
Store at 25°C (77°F); excursions permitted to 15°-30°C (59°-86°F) [see USP Controlled Room Temperature]. Keep container tightly closed, and protect from moisture and humidity.

17 PATIENT COUNSELING INFORMATION

Advise the patient to read the FDA-approved patient labeling (Medication Guide).

- Congestive Heart Failure: Inform patients of the signs and symptoms of heart failure. Instruct patients who experience an unusually rapid increase in weight or edema, shortness of breath, or other symptoms of heart failure while on ACTOPLUS MET to immediately report these symptoms to their healthcare provider. [see Warnings and Precautions (5.1)].
- Lactic Acidosis: Explain to patients the risks of lactic acidosis, its symptoms and conditions that predispose to its development, as noted in the Warnings and Precautions (5.2) section. Advise patients to discontinue ACTOPLUS MET immediately and to promptly notify their healthcare professional if unexplained hyperventilation, myalgia, gastrointestinal symptoms, malaise, unusual somnolence, or other nonspecific symptoms occur.
  Counsel patients against excessive alcohol intake and inform patients about the importance of regular testing of renal function while receiving ACTOPLUS MET.
  Inform patients about the importance of regular testing of renal function and hematologic parameters when receiving treatment with ACTOPLUS MET
  Instruct patients to inform their doctor that they are taking ACTOPLUS MET prior to any surgical or radiological procedure, as temporary discontinuation of ACTOPLUS MET may be required until renal function has been confirmed to be normal.
- Edema: Inform patients that ACTOPLUS MET use can lead to new-onset or worsening of edema. Instruct patients to immediately report symptoms of rapid weight increase or worsening edema to their healthcare provider [see Warnings and Precautions (5.3)].
- Hypoglycemia with Concomitant Use with Insulin or Insulin Secretagogues: Inform patients that the risk of hypoglycemia is increased when ACTOPLUS MET is used with insulin or insulin secretagogues (such as a sulfonylurea). Educate patients on the signs and symptoms of hypoglycemia [see Warnings and Precautions (5.4)].
- Hepatic Effects: Instruct patients to promptly stop taking ACTOPLUS MET and seek immediate medical advice if they experience signs or symptoms of liver injury (e.g., unexplained nausea, vomiting, abdominal pain, fatigue, anorexia, or dark urine) [see Warnings and Precautions (5.5)].
- Urinary Bladder Tumors: Advise patients to promptly report any hematuria, dysuria or urinary urgency that develops or increases during treatment as these may be due to bladder cancer [see Warnings and Precautions (5.6)].
- Fractures: Inform female patients about the risk of fractures while taking ACTOPLUS MET. Provide them with information on factors that may contribute to fracture risk [see Warnings and Precautions (5.7)].
- Macular Edema: Educate patients on the signs and symptoms of macular edema and advise them to seek medical attention from an ophthalmologist if they experience symptoms of macular edema [see Warnings and Precautions (5.8)].
- Vitamin B12 Levels: Inform patients about the importance of obtaining regular hematological laboratory monitoring while receiving ACTOPLUS MET [see Warnings and Precautions (5.9)].
- Females of Reproductive Age: Inform female patients that treatment with ACTOPLUS MET may result in an unintended pregnancy in some premenopausal anovulatory females due to its effect on ovulation [see Use in Specific Populations (8.3)]
- Missed Dosage: Instruct patients if a dose is missed, not to double their next dose.

Distributed by:
Takeda Pharmaceuticals America, Inc.
Cambridge, MA 02142

ACTOS and ACTOPLUS MET are registered trademarks of Takeda Pharmaceutical Company Limited.

©2025 Takeda Pharmaceuticals America, Inc. All rights reserved.

APM001 R18

MEDICATION GUIDE
ACTOPLUS MET® (ak-TŌ-plus-met)
(pioglitazone and metformin hydrochloride)
tablets

Read this Medication Guide carefully before you start taking ACTOPLUS MET and each time you get a refill. There may be new information. This information does not take the place of talking with your healthcare provider about your medical condition or your treatment. If you have any questions about ACTOPLUS MET, ask your healthcare provider or pharmacist.

What is the most important information I should know about ACTOPLUS MET?

ACTOPLUS MET can cause serious side effects, including:

- Heart failure. Pioglitazone, one of the medicines in ACTOPLUS MET, can cause your body to keep extra fluid (fluid retention), which leads to swelling (edema) and weight gain. Extra body fluid can make some heart problems worse or lead to heart failure. Heart failure means your heart does not pump blood well enough.
  Before you start taking ACTOPLUS MET:
  Tell your healthcare provider if you have ever had heart failure or have problems with your kidneys
  Call your healthcare provider right away if you have any of the following:
  - increasing shortness of breath or trouble breathing, especially when you lie down
  - an unusually fast increase in weight
  - swelling or fluid retention, especially in the ankles or legs
  - unusual tiredness

These may be symptoms of heart failure.

- Lactic acidosis. Metformin, one of the medicines in ACTOPLUS MET, can cause a rare but serious condition called lactic acidosis (a buildup of an acid in the blood) that can cause death. Lactic acidosis is a medical emergency and must be treated in the hospital.
  Stop taking ACTOPLUS MET and call your healthcare provider right away if you have any of the following symptoms, which could be signs of lactic acidosis:
  - feel very weak or tired
  - have unusual (not normal) muscle pain
  - have trouble breathing
  - have unusual sleepiness or sleep longer than usual
  - have unexplained stomach or intestinal problems with nausea, vomiting, or diarrhea
  - feel cold, especially in your arms and legs
  - feel dizzy or lightheaded
  - have a slow or irregular heartbeat
    Most people who have had lactic acidosis with metformin have other things that, combined with the metformin, led to the lactic acidosis. Tell your healthcare provider if you have any of the following, because you have a higher chance for getting lactic acidosis with ACTOPLUS MET if you:
  - have severe kidney problems or your kidneys are affected by certain x-ray tests that use injectable dye.
  - have liver problems
  - drink alcohol very often, or drink a lot of alcohol in short-term ("binge" drinking)
  - get dehydrated (lose a large amount of body fluids). This can happen if you are sick with a fever, vomiting, or diarrhea. Dehydration can also happen when you sweat a lot with activity or exercise and do not drink enough fluids
  - have surgery
  - have a heart attack, severe infection, or stroke
  - are 65 years of age or older

The best way to keep from having a problem with lactic acidosis from metformin is to tell your healthcare provider if you have any of the problems in the list above. Your healthcare provider may decide to stop your ACTOPLUS MET for a while if you have any of these things.

ACTOPLUS MET can have other serious side effects. See “What are the possible side effects of ACTOPLUS MET?”.

What is ACTOPLUS MET?

ACTOPLUS MET is a prescription medicine that contains 2 diabetes medicines, pioglitazone (ACTOS®) and metformin hydrochloride (GLUCOPHAGE). ACTOPLUS MET is used along with diet and exercise to improve blood sugar (glucose) control in adults with type 2 diabetes.

ACTOPLUS MET is not for people with type 1 diabetes.

ACTOPLUS MET is not for people with diabetic ketoacidosis (increased ketones in your blood or urine).

It is not known if ACTOPLUS MET is safe and effective in children under the age of 18. ACTOPLUS MET is not recommended for use in children.

Who should not take ACTOPLUS MET?

See “What is the most important information I should know about ACTOPLUS MET?”.

Do not take ACTOPLUS MET if you:

- have severe heart failure
- have severe kidney problems
- have a condition called acute or chronic metabolic acidosis, including diabetic ketoacidosis.
- are allergic to pioglitazone, metformin, or any of the ingredients in ACTOPLUS MET or have had a serious allergic (hypersensitivity) reaction to pioglitazone or metformin. See the end of this Medication Guide for a complete list of ingredients in ACTOPLUS MET. Symptoms of a serious allergic reaction to ACTOPLUS MET may include:

- swelling of your face, lips, throat and other areas on your skin
- raised, red areas on your skin (hives)

- difficulty with swallowing or breathing
- skin rash, itching, flaking or peeling

If you have these symptoms, stop taking ACTOPLUS MET and contact your healthcare provider or go to the nearest hospital emergency room right away.

Tell your healthcare provider before taking ACTOPLUS MET if you have any of these conditions.

What should I tell my healthcare provider before taking ACTOPLUS MET?

Before you take ACTOPLUS MET, tell your healthcare provider if you:

- have heart failure
- have kidney or liver problems
- are going to have dye injected into a vein for an x-ray, CAT scan, heart study, or other type of scanning
- will be undergoing a surgical procedure
- drink a lot of alcohol (all the time or short binge drinking)
- have type 1 ("juvenile") diabetes or had diabetic ketoacidosis
- have a type of diabetic eye disease that causes swelling in the back of the eye (macular edema)
- have low levels of vitamin B12 in your blood
- have or have had cancer of the bladder
- are pregnant or plan to become pregnant. It is not known if ACTOPLUS MET can harm your unborn baby. Talk to your healthcare provider if you are pregnant or plan to become pregnant about the best way to control your blood glucose levels while pregnant
- are a woman who has not gone through menopause (premenopausal), who does not have periods regularly or at all. ACTOPLUS MET may increase your chance of becoming pregnant.
  Talk to your healthcare provider about birth control choices while taking ACTOPLUS MET. Tell your healthcare provider right away if you become pregnant while taking ACTOPLUS MET
- are breastfeeding or plan to breastfeed. It is not known if ACTOPLUS MET passes into your milk and if it can harm your baby. Talk to your healthcare provider about the best way to control your blood glucose levels while breastfeeding

Tell your healthcare provider about all the medicines you take, including prescription and over the counter medicines, vitamins, and herbal supplements.

Know the medicines you take. Keep a list of your medicines and show it to your healthcare provider and pharmacist before you start a new medicine. They will tell you if it is okay to take ACTOPLUS MET with other medicines.

ACTOPLUS MET may affect the way other medicines work, and other medicines may affect how ACTOPLUS MET works. Contact your healthcare provider before you start or stop other types of medicines.

How should I take ACTOPLUS MET?

- Take ACTOPLUS MET exactly as your healthcare provider tells you to take it
- Your healthcare provider may need to change your dose of ACTOPLUS MET. Do not change your ACTOPLUS MET dose unless your healthcare provider tells you to
- Take ACTOPLUS MET with meals to lower your chance of an upset stomach
- If you miss a dose of ACTOPLUS MET, take your next dose as prescribed unless your healthcare provider tells you differently. Do not take two doses at one time the next day
- If you take too much ACTOPLUS MET, call your healthcare provider or go to the nearest hospital emergency room right away
- If your body is under stress such as from a fever, infection, accident, or surgery, the dose of your diabetes medicines may need to be changed. Call your healthcare provider right away
- Stay on your diet and exercise programs and test your blood sugar regularly while taking ACTOPLUS MET
- Your healthcare provider should do certain blood tests before you start and while you take ACTOPLUS MET
- Your healthcare provider should also do hemoglobin A1C testing to check how well your blood sugar is controlled with ACTOPLUS MET
- Your healthcare provider should check your eyes regularly while you take ACTOPLUS MET

What are the possible side effects of ACTOPLUS MET?

ACTOPLUS MET may cause serious side effects, including:

- See “What is the most important information I should know about ACTOPLUS MET?”.
- Low blood sugar (hypoglycemia). If you take ACTOPLUS MET with another medicine that can cause low blood sugar, such as a sulfonylurea or insulin, your risk of getting low blood sugar is higher. The dose of your sulfonylurea medicine or insulin may need to be lowered while you take ACTOPLUS MET. Signs and symptoms of low blood sugar may include:
  - shaking or feeling jittery ∘ sweating ∘ fast heartbeat
  - change in vision ∘ hunger ∘ headache
  - change in mood ∘ confusion ∘ dizziness
- Liver problems. Call your healthcare provider right away or go to the nearest hospital emergency room if you have unexplained symptoms such as:
  - nausea or vomiting
  - stomach pain
  - unusual or unexplained tiredness
  - loss of appetite
  - dark urine
  - yellowing of your skin or the whites of your eyes
- Bladder tumors. There may be an increased chance of having bladder cancer when you take ACTOPLUS MET. You should not take ACTOPLUS MET if you are receiving treatment for bladder cancer. Tell your healthcare provider right away if you have any of the following symptoms of bladder cancer:
  - blood or a red color in your urine
  - an increased need to urinate
  - pain while you urinate
- Broken bones (fractures). Usually in the hand, upper arm, or foot in women. Talk to your healthcare provider for advice on how to keep your bones healthy
- Diabetic eye disease with swelling in the back of the eye (macular edema). Tell your healthcare provider right away if you have any changes in your vision. Your healthcare provider should check your eyes regularly
- Release of an egg from an ovary in a woman (ovulation) leading to pregnancy. Ovulation may happen when premenopausal women who do not have regular monthly periods take ACTOPLUS MET. This can increase your chance of getting pregnant.
- Low vitamin B12 (vitamin B12 deficiency). Using metformin, one of the medicines in ACTOPLUS MET for long periods of time may cause a decrease in the amount of vitamin B12 in your blood, especially if you have had low vitamin B12 levels before. Your healthcare provider may do blood tests to check your vitamin B12 levels. The most common side effects of ACTOPLUS MET include:
  - cold-like symptoms (upper respiratory tract infection)
  - swelling (edema)
  - diarrhea
  - headache
  - increased weight

Tell your healthcare provider if you have any side effect that bothers you or that does not go away. These are not all the side effects of ACTOPLUS MET. For more information, ask your healthcare provider or pharmacist.

Call your doctor for medical advice about side effects. You may report side effects to FDA at 1-800-FDA-1088.

How should I store ACTOPLUS MET?

- Store ACTOPLUS MET at 68°F to 77°F (20°C to 25°C).
- Keep ACTOPLUS MET in the original container and protect from light.
- Keep the ACTOPLUS MET bottle tightly closed and keep tablets dry.

Keep ACTOPLUS MET and all medicines out of the reach of children.

General information about the safe and effective use of ACTOPLUS MET

Medicines are sometimes prescribed for purposes other than those listed in a Medication Guide. Do not use ACTOPLUS MET for a condition for which it was not prescribed. Do not give ACTOPLUS MET to other people, even if they have the same symptoms you have. It may harm them.

You can ask your healthcare provider or pharmacist for information about ACTOPLUS MET that is written for health professionals.

What are the ingredients in ACTOPLUS MET?

Active Ingredients: pioglitazone hydrochloride and metformin hydrochloride

Inactive Ingredients: povidone, microcrystalline cellulose, croscarmellose sodium, magnesium stearate, hypromellose 2910, polyethylene glycol 8000, titanium dioxide, and talc.

Distributed by:
Takeda Pharmaceuticals America, Inc.
Cambridge, MA 02142

ACTOS and ACTOPLUS MET are registered trademarks of Takeda Pharmaceutical Company Limited.

©2025 Takeda Pharmaceuticals America, Inc. All rights reserved.

For more information, go to www.actoplusmet.com or call 1-877-825-3327.

This Medication Guide has been approved by the U.S. Food and Drug Administration.
APM001 R18

Revised: 3/2025

PRINCIPAL DISPLAY PANEL - 15 mg/850 mg Tablet Bottle Label

NDC 64764-158-60
60 Tablets

actoplus met®

pioglitazone 15 mg and
metformin HCl 850 mg tablets

Each film-coated tablet contains
pioglitazone hydrochloride
equivalent to 15 mg pioglitazone
and 850 mg metformin HCl.

Dispense with Medication Guide
available in package insert or at
www.actoplusmet.com

Takeda

Rx Only